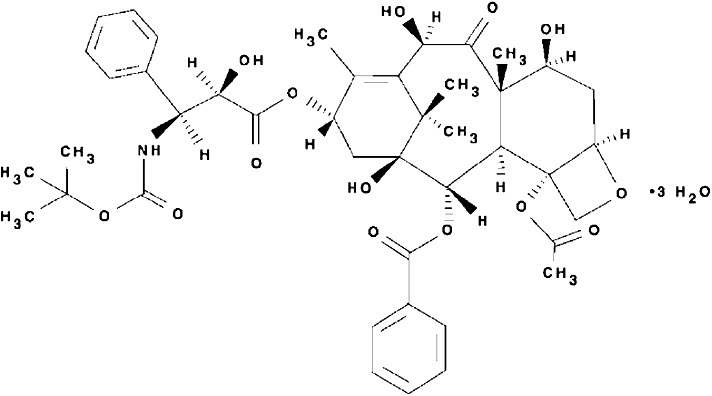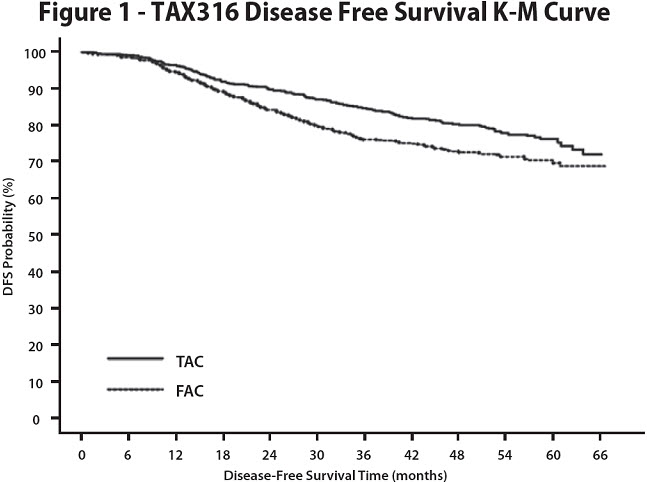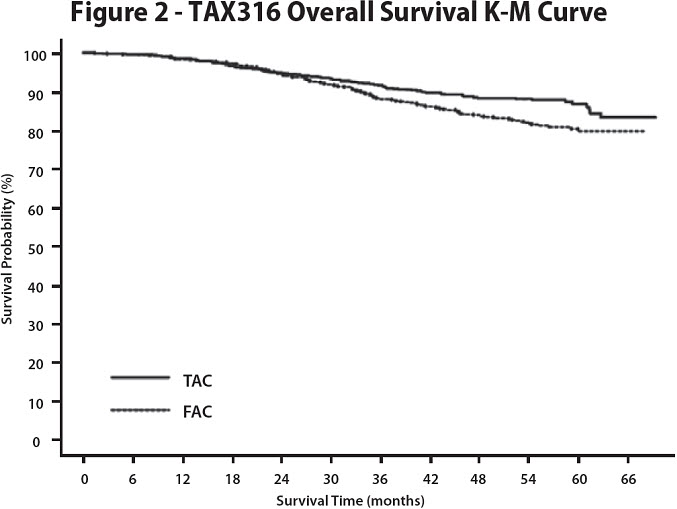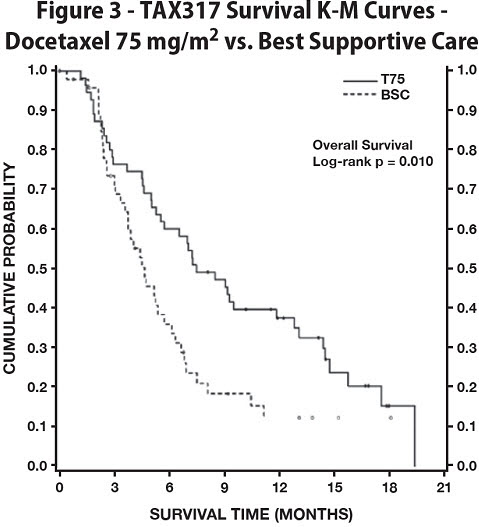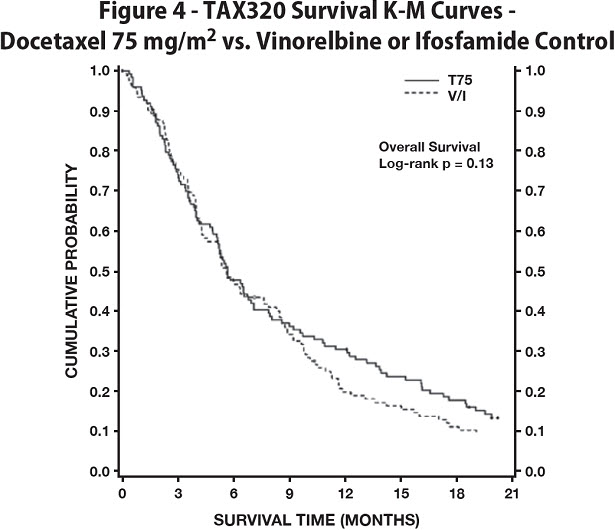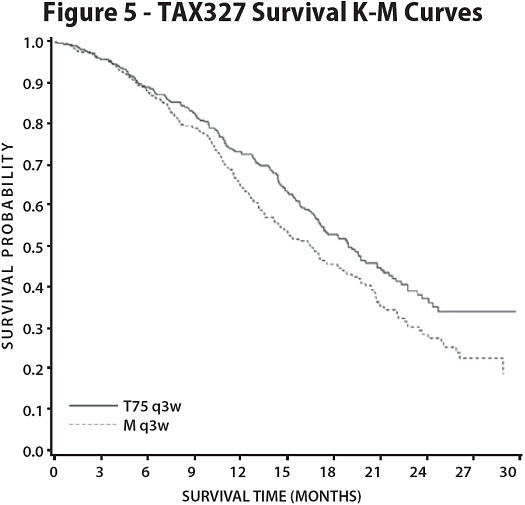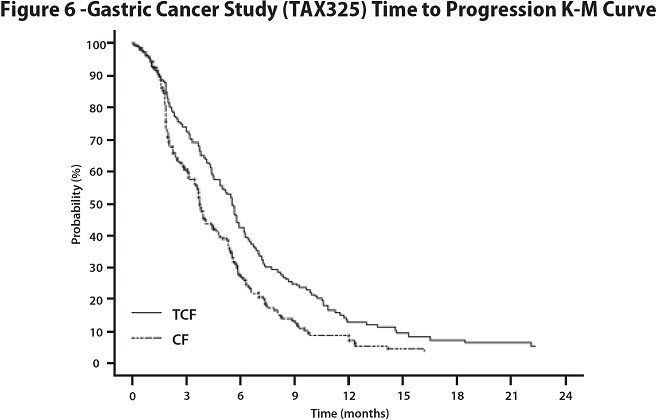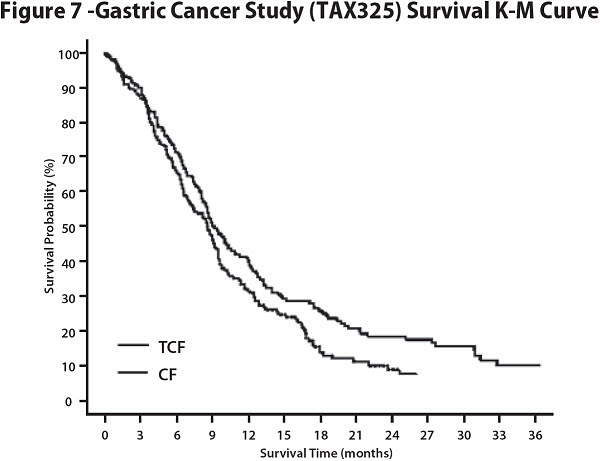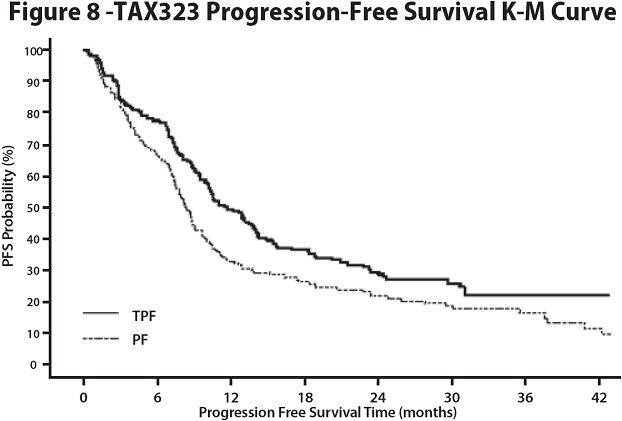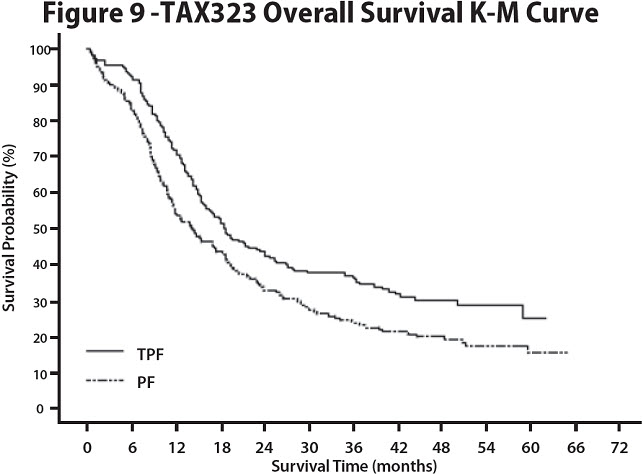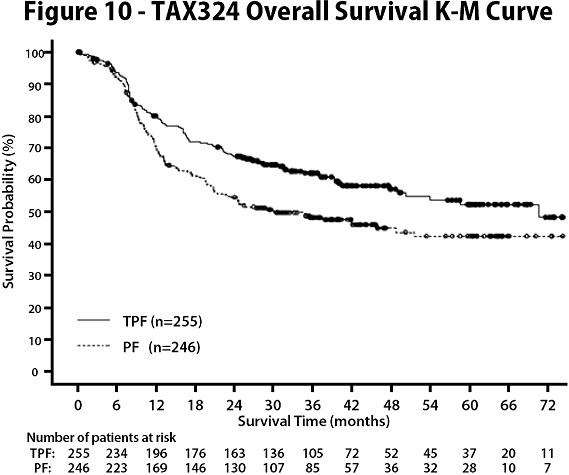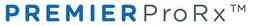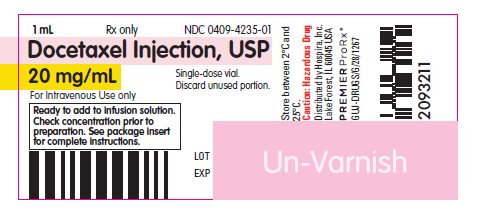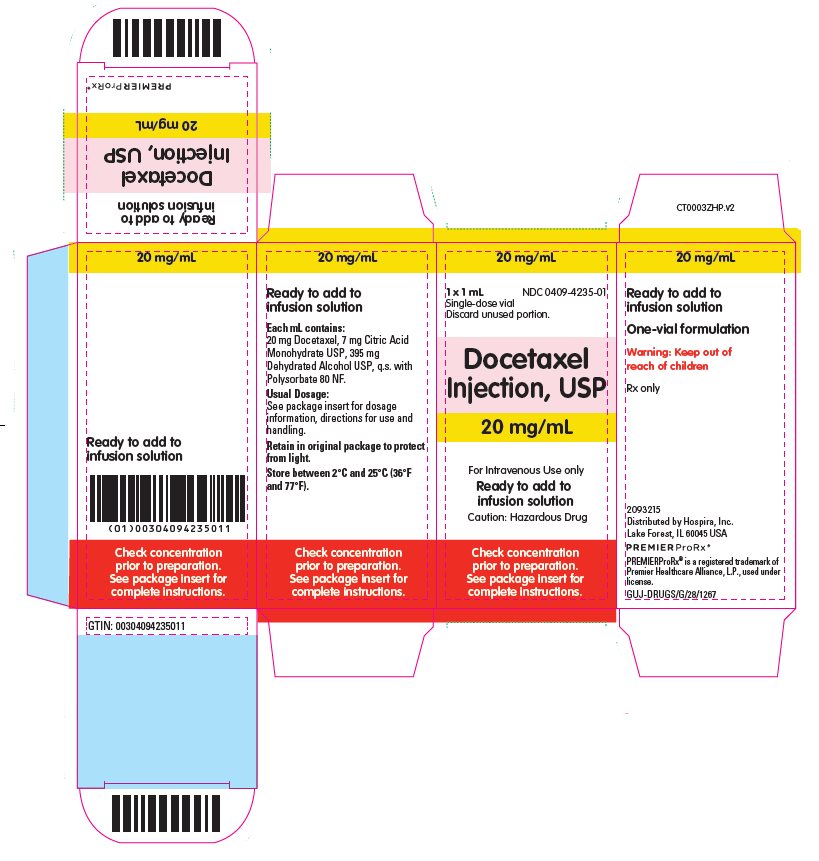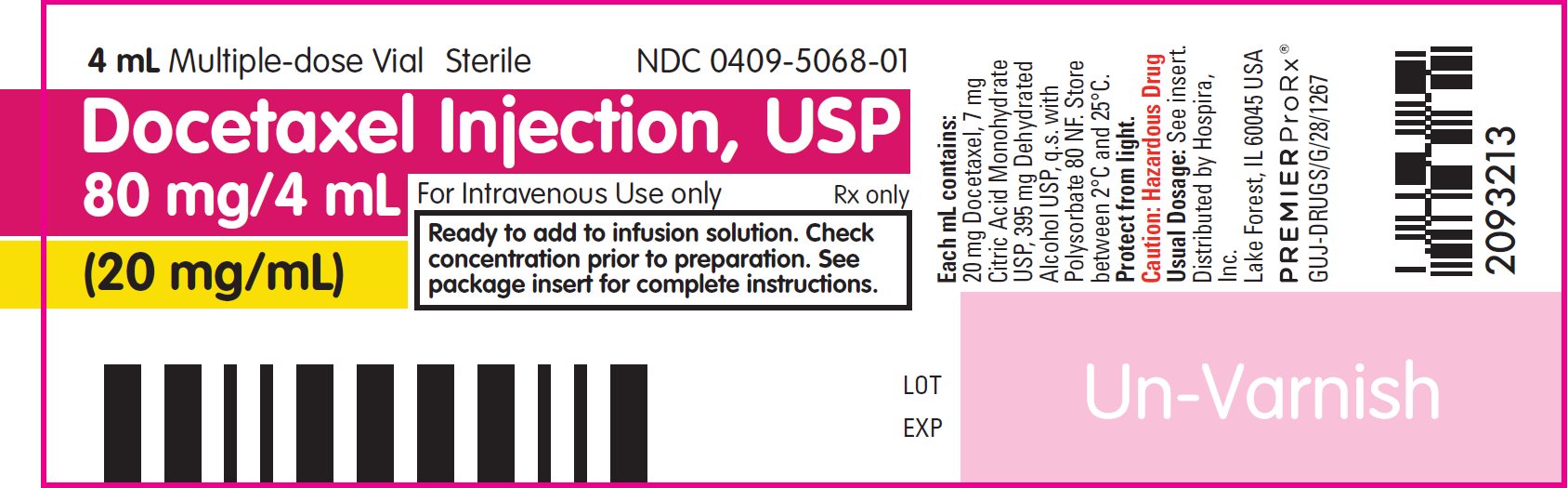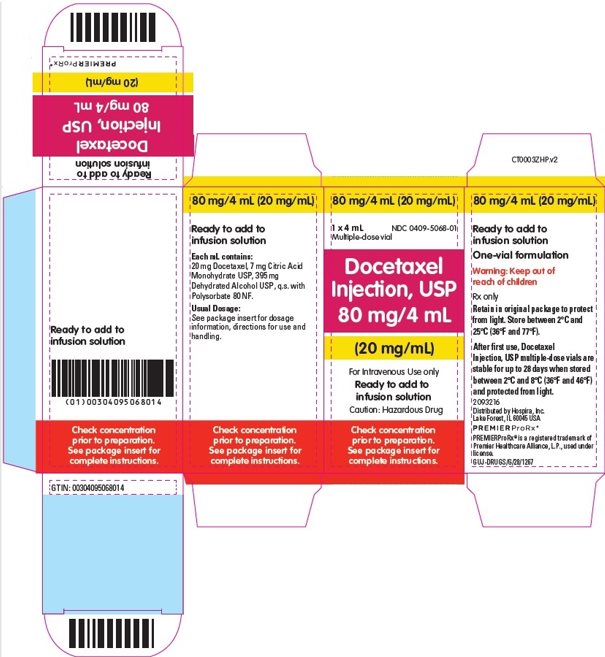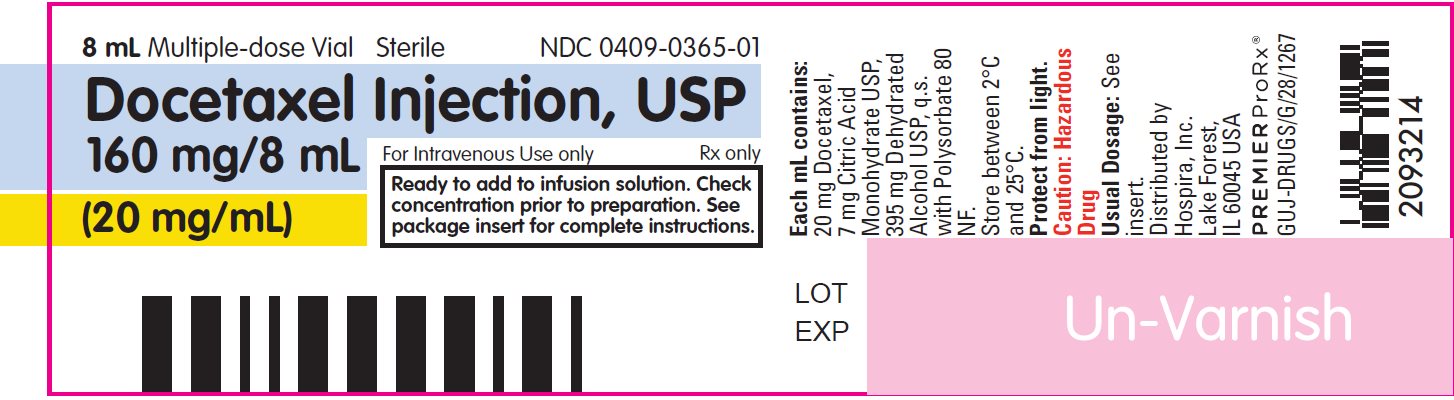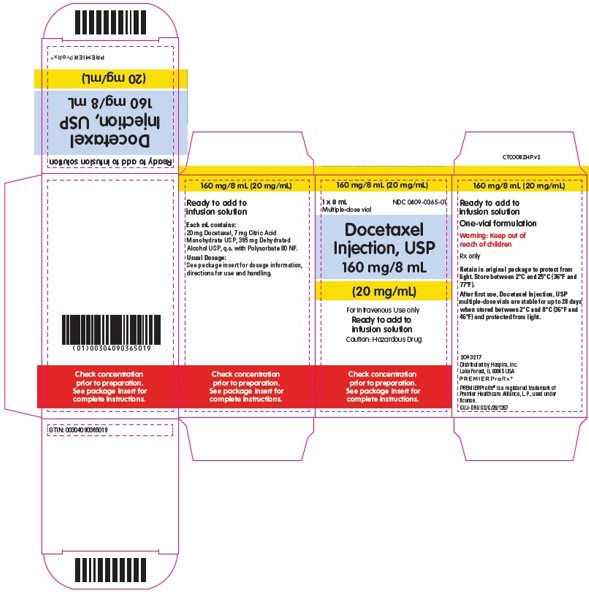 DRUG LABEL: Docetaxel
NDC: 0409-4235 | Form: INJECTION, SOLUTION
Manufacturer: Hospira, Inc.
Category: prescription | Type: HUMAN PRESCRIPTION DRUG LABEL
Date: 20250131

ACTIVE INGREDIENTS: DOCETAXEL 20 mg/1 mL
INACTIVE INGREDIENTS: POLYSORBATE 80 520 mg/1 mL; CITRIC ACID MONOHYDRATE 7 mg/1 mL; ALCOHOL 395 mg/1 mL

HIGHLIGHTS OF PRESCRIBING INFORMATION

These highlights do not include all the information needed to use DOCETAXEL INJECTION safely and effectively. See full prescribing information for DOCETAXEL INJECTION.
DOCETAXEL injection, for intravenous use
Initial U.S. Approval: 1996

WARNING: TOXIC DEATHS, HEPATOTOXICITY, NEUTROPENIA, HYPERSENSITIVITY REACTIONS, and FLUID RETENTION

See full prescribing information for complete boxed warning.

- Treatment-related mortality increases with abnormal liver function, at higher doses, and in patients with NSCLC and prior platinum-based therapy receiving docetaxel at 100 mg/m^2 (5.1)
- Avoid use of Docetaxel Injection if bilirubin > ULN, or if AST and/or ALT >1.5 × ULN concomitant with alkaline phosphatase >2.5 × ULN. LFT elevations increase risk of severe or life-threatening complications. Obtain LFTs before each treatment cycle (5.2)
- Do not administer Docetaxel Injection to patients with neutrophil counts <1500 cells/mm^3. Obtain frequent blood counts to monitor for neutropenia (4, 5.3)
- Severe hypersensitivity, including fatal anaphylaxis, has been reported in patients who received dexamethasone premedication. Severe reactions require immediate discontinuation of Docetaxel Injection and administration of appropriate therapy (5.5)
- Contraindicated if history of severe hypersensitivity reactions to docetaxel or to drugs formulated with polysorbate 80 (4)
- Severe fluid retention may occur despite dexamethasone (5.6)

1 INDICATIONS AND USAGE

Docetaxel Injection is a microtubule inhibitor indicated for:

- Breast Cancer (BC): single agent for locally advanced or metastatic BC after chemotherapy failure; and with doxorubicin and cyclophosphamide as adjuvant treatment of operable node-positive BC (1.1)
- Non-small Cell Lung Cancer (NSCLC): single agent for locally advanced or metastatic NSCLC after platinum therapy failure; and with cisplatin for unresectable, locally advanced or metastatic untreated NSCLC (1.2)
- Castration-Resistant Prostate Cancer (CRPC): with prednisone in metastatic castration-resistant prostate cancer (1.3)
- Gastric Adenocarcinoma (GC): with cisplatin and fluorouracil for untreated, advanced GC, including the gastroesophageal junction (1.4)
- Squamous Cell Carcinoma of the Head and Neck (SCCHN): with cisplatin and fluorouracil for induction treatment of locally advanced SCCHN (1.5)

2 DOSAGE AND ADMINISTRATION

Administer in a facility equipped to manage possible complications (e.g., anaphylaxis). Administer intravenously (IV) over 1 hour every 3 weeks. PVC equipment is not recommended. Use only a 21 gauge needle to withdraw Docetaxel Injection from the vial.

- BC locally advanced or metastatic: 60 mg/m^2 to 100 mg/m^2 single agent (2.1)
- BC adjuvant: 75 mg/m^2 administered 1 hour after doxorubicin 50 mg/m^2 and cyclophosphamide 500 mg/m^2 every 3 weeks for 6 cycles (2.1)
- NSCLC: after platinum therapy failure: 75 mg/m^2 single agent (2.2)
- NSCLC: chemotherapy-naïve: 75 mg/m^2 followed by cisplatin 75 mg/m^2 (2.2)
- CRPC: 75 mg/m^2 with 5 mg prednisone twice a day continuously (2.3)
- GC: 75 mg/m^2 followed by cisplatin 75 mg/m^2 (both on day 1 only) followed by fluorouracil 750 mg/m^2 per day as a 24-hour IV (days 1–5), starting at end of cisplatin infusion (2.4)
- SCCHN: 75 mg/m^2 followed by cisplatin 75 mg/m^2 IV (day 1), followed by fluorouracil 750 mg/m^2 per day as a 24-hour IV (days 1–5), starting at end of cisplatin infusion; for 4 cycles (2.5)
- SCCHN: 75 mg/m^2 followed by cisplatin 100 mg/m^2 IV (day 1), followed by fluorouracil 1000 mg/m^2 per day as a 24-hour IV (days 1–4); for 3 cycles (2.5)

For all patients:

- Premedicate with oral corticosteroids (2.6)
- Adjust dose as needed (2.7)

3 DOSAGE FORMS AND STRENGTHS

- 20 mg/mL single-dose vial (3)
- 80 mg/4 mL (20 mg/mL) multiple-dose vial (3)
- 160 mg/8 mL (20 mg/mL) multiple-dose vial (3)

4 CONTRAINDICATIONS

- Hypersensitivity to docetaxel or polysorbate 80 (4)
- Neutrophil counts of <1500 cells/mm^3 (4)

5 WARNINGS AND PRECAUTIONS

- Second primary malignancies: In patients treated with Docetaxel Injection-containing regimens, monitor for delayed AML, MDS, NHL, and renal cancer. (5.7)
- Cutaneous reactions: Reactions including erythema of the extremities with edema followed by desquamation may occur. Severe cutaneous adverse reactions have been reported. Severe skin toxicity may require dose adjustment or permanent treatment discontinuation. (5.8)
- Neurologic reactions: Reactions including paresthesia, dysesthesia, and pain may occur. Severe neurosensory symptoms require dose adjustment or discontinuation if persistent. (5.9)
- Eye disorders: Cystoid macular edema (CME) has been reported and requires treatment discontinuation. (5.10)
- Asthenia: Severe asthenia may occur and may require treatment discontinuation. (5.11)
- Embryo-fetal toxicity: Can cause fetal harm. Advise patients of the potential risk to a fetus and to use effective contraception. (5.12, 8.1, 8.3)
- Alcohol content: The alcohol content in a dose of Docetaxel Injection may affect the central nervous system. This may include impairment of a patient's ability to drive or use machines immediately after infusion. (5.13)
- Tumor lysis syndrome: Tumor lysis syndrome has been reported. Patients at risk should be well hydrated and closely monitored during treatment. (5.14)

6 ADVERSE REACTIONS

Most common adverse reactions across all docetaxel indications are infections, neutropenia, anemia, febrile neutropenia, hypersensitivity, thrombocytopenia, neuropathy, dysgeusia, dyspnea, constipation, anorexia, nail disorders, fluid retention, asthenia, pain, nausea, diarrhea, vomiting, mucositis, alopecia, skin reactions, and myalgia. (6)
To report SUSPECTED ADVERSE REACTIONS, contact Hospira, Inc. at 1-800-441-4100 or FDA at 1-800-FDA-1088 or www.fda.gov/medwatch.

7 DRUG INTERACTIONS

- Cytochrome P450 3A4 inducers, inhibitors, or substrates: May alter docetaxel metabolism. (7)

8 USE IN SPECIFIC POPULATIONS

- Lactation: Advise women not to breastfeed. (8.2)
- Females and Males of Reproductive Potential: Verify pregnancy status of females prior to initiation of Docetaxel Injection. (8.3)

FULL PRESCRIBING INFORMATION

WARNING: TOXIC DEATHS, HEPATOTOXICITY, NEUTROPENIA, HYPERSENSITIVITY REACTIONS, and FLUID RETENTION

Treatment-related mortality associated with docetaxel is increased in patients with abnormal liver function, in patients receiving higher doses, and in patients with non-small cell lung carcinoma and a history of prior treatment with platinum-based chemotherapy who receive docetaxel as a single agent at a dose of 100 mg/m^2 [see Warnings and Precautions (5.1)].

Avoid the use of Docetaxel Injection in patients with bilirubin > upper limit of normal (ULN), or to patients with AST and/or ALT >1.5 × ULN concomitant with alkaline phosphatase >2.5 × ULN. Patients with elevations of bilirubin or abnormalities of transaminase concurrent with alkaline phosphatase are at increased risk for the development of severe neutropenia, febrile neutropenia, infections, severe thrombocytopenia, severe stomatitis, severe skin toxicity, and toxic death. Patients with isolated elevations of transaminase >1.5 × ULN also had a higher rate of febrile neutropenia. Measure bilirubin, AST or ALT, and alkaline phosphatase prior to each cycle of Docetaxel Injection [see Warnings and Precautions (5.2)].

Do not administer Docetaxel Injection to patients with neutrophil counts of <1500 cells/mm^3. Monitor blood counts frequently as neutropenia may be severe and result in infection [see Warnings and Precautions (5.3)].

Do not administer Docetaxel Injection to patients who have a history of severe hypersensitivity reactions to docetaxel or to other drugs formulated with polysorbate 80 [see Contraindications (4)]. Severe hypersensitivity reactions have been reported in patients despite dexamethasone premedication. Hypersensitivity reactions require immediate discontinuation of the Docetaxel Injection infusion and administration of appropriate therapy [see Warnings and Precautions (5.5)].

Severe fluid retention occurred in 6.5% (6/92) of patients despite use of dexamethasone premedication. It was characterized by one or more of the following events: poorly tolerated peripheral edema, generalized edema, pleural effusion requiring urgent drainage, dyspnea at rest, cardiac tamponade, or pronounced abdominal distention (due to ascites) [see Warnings and Precautions (5.6)].

1 INDICATIONS AND USAGE

1.1 Breast Cancer

Docetaxel Injection is indicated for the treatment of patients with locally advanced or metastatic breast cancer after failure of prior chemotherapy.

Docetaxel Injection in combination with doxorubicin and cyclophosphamide is indicated for the adjuvant treatment of patients with operable node-positive breast cancer.

1.2 Non-small Cell Lung Cancer

Docetaxel Injection as a single agent is indicated for the treatment of patients with locally advanced or metastatic non-small cell lung cancer after failure of prior platinum-based chemotherapy.

Docetaxel Injection in combination with cisplatin is indicated for the treatment of patients with unresectable, locally advanced or metastatic non-small cell lung cancer who have not previously received chemotherapy for this condition.

1.3 Prostate Cancer

Docetaxel Injection in combination with prednisone is indicated for the treatment of patients with metastatic castration-resistant prostate cancer.

1.4 Gastric Adenocarcinoma

Docetaxel Injection in combination with cisplatin and fluorouracil is indicated for the treatment of patients with advanced gastric adenocarcinoma, including adenocarcinoma of the gastroesophageal junction, who have not received prior chemotherapy for advanced disease.

1.5 Head and Neck Cancer

Docetaxel Injection in combination with cisplatin and fluorouracil is indicated for the induction treatment of patients with locally advanced squamous cell carcinoma of the head and neck (SCCHN).

2 DOSAGE AND ADMINISTRATION

For all indications, toxicities may warrant dosage adjustments [see Dosage and Administration (2.7)].

Administer in a facility equipped to manage possible complications (e.g., anaphylaxis).

2.1 Breast Cancer

- For locally advanced or metastatic breast cancer after failure of prior chemotherapy, the recommended dose of Docetaxel Injection is 60 mg/m^2 to 100 mg/m^2 administered intravenously over 1 hour every 3 weeks.
- For the adjuvant treatment of operable node-positive breast cancer, the recommended Docetaxel Injection dose is 75 mg/m^2 administered 1 hour after doxorubicin 50 mg/m^2 and cyclophosphamide 500 mg/m^2 every 3 weeks for 6 courses. Prophylactic G-CSF may be used to mitigate the risk of hematological toxicities [see Dosage and Administration (2.7)].

2.2 Non-small Cell Lung Cancer

- For treatment after failure of prior platinum-based chemotherapy, docetaxel was evaluated as monotherapy, and the recommended dose is 75 mg/m^2 administered intravenously over 1 hour every 3 weeks. A dose of 100 mg/m^2 in patients previously treated with chemotherapy was associated with increased hematologic toxicity, infection, and treatment-related mortality in randomized controlled trials [see Boxed Warning, Dosage and Administration (2.7), Warnings and Precautions (5), Clinical Studies (14)].
- For chemotherapy-naïve patients, docetaxel was evaluated in combination with cisplatin. The recommended dose of Docetaxel Injection is 75 mg/m^2 administered intravenously over 1 hour immediately followed by cisplatin 75 mg/m^2 over 30–60 minutes every 3 weeks [see Dosage and Administration (2.7)].

2.3 Prostate Cancer

- For metastatic castration-resistant prostate cancer, the recommended dose of Docetaxel Injection is 75 mg/m^2 every 3 weeks as a 1 hour intravenous infusion. Prednisone 5 mg orally twice daily is administered continuously [see Dosage and Administration (2.7)].

2.4 Gastric Adenocarcinoma

- For gastric adenocarcinoma, the recommended dose of Docetaxel Injection is 75 mg/m^2 as a 1 hour intravenous infusion, followed by cisplatin 75 mg/m^2, as a 1 to 3 hour intravenous infusion (both on day 1 only), followed by fluorouracil 750 mg/m^2 per day given as a 24-hour continuous intravenous infusion for 5 days, starting at the end of the cisplatin infusion. Treatment is repeated every three weeks. Patients must receive premedication with antiemetics and appropriate hydration for cisplatin administration [see Dosage and Administration (2.7)].

2.5 Head and Neck Cancer

Patients must receive premedication with antiemetics, and appropriate hydration (prior to and after cisplatin administration). Prophylaxis for neutropenic infections should be administered. All patients treated on the Docetaxel Injection containing arms of the TAX323 and TAX324 studies received prophylactic antibiotics.

Induction Chemotherapy Followed by Radiotherapy (TAX323)

For the induction treatment of locally advanced inoperable SCCHN, the recommended dose of Docetaxel Injection is 75 mg/m^2 as a 1 hour intravenous infusion followed by cisplatin 75 mg/m^2 intravenously over 1 hour, on day one, followed by fluorouracil as a continuous intravenous infusion at 750 mg/m^2 per day for five days. This regimen is administered every 3 weeks for 4 cycles. Following chemotherapy, patients should receive radiotherapy [see Dosage and Administration (2.7)].

Induction Chemotherapy Followed by Chemoradiotherapy (TAX324)

For the induction treatment of patients with locally advanced (unresectable, low surgical cure, or organ preservation) SCCHN, the recommended dose of Docetaxel Injection is 75 mg/m^2 as a 1 hour intravenous infusion on day 1, followed by cisplatin 100 mg/m^2 administered as a 30-minute to 3 hour infusion, followed by fluorouracil 1000 mg/m^2/day as a continuous infusion from day 1 to day 4. This regimen is administered every 3 weeks for 3 cycles. Following chemotherapy, patients should receive chemoradiotherapy [see Dosage and Administration (2.7)].

2.6 Premedication Regimen

All patients should be premedicated with oral corticosteroids (see below for prostate cancer) such as dexamethasone 16 mg per day (e.g., 8 mg twice daily) for 3 days starting 1 day prior to Docetaxel Injection administration in order to reduce the incidence and severity of fluid retention as well as the severity of hypersensitivity reactions [see Boxed Warning, Warnings and Precautions (5.5)].

For metastatic castration-resistant prostate cancer, given the concurrent use of prednisone, the recommended premedication regimen is oral dexamethasone 8 mg at 12 hours, 3 hours, and 1 hour before the Docetaxel Injection infusion [see Warnings and Precautions (5.5)].

2.7 Dosage Adjustments during Treatment

Breast Cancer

Patients who are dosed initially at 100 mg/m^2 and who experience either febrile neutropenia, neutrophils <500 cells/mm^3 for more than 1 week, or severe or cumulative cutaneous reactions during Docetaxel Injection therapy should have the dosage adjusted from 100 mg/m^2 to 75 mg/m^2. If the patient continues to experience these reactions, the dosage should either be decreased from 75 mg/m^2 to 55 mg/m^2 or the treatment should be discontinued. Conversely, patients who are dosed initially at 60 mg/m^2 and who do not experience febrile neutropenia, neutrophils <500 cells/mm^3 for more than 1 week, severe or cumulative cutaneous reactions, or severe peripheral neuropathy during Docetaxel Injection therapy may tolerate higher doses. Patients who develop ≥grade 3 peripheral neuropathy should have Docetaxel Injection treatment discontinued entirely.

Combination Therapy with Docetaxel Injection in the Adjuvant Treatment of Breast Cancer

Docetaxel Injection in combination with doxorubicin and cyclophosphamide should be administered when the neutrophil count is ≥1500 cells/mm^3. Patients who experience febrile neutropenia should receive G-CSF in all subsequent cycles. Patients who continue to experience this reaction should remain on G-CSF and have their Docetaxel Injection dose reduced to 60 mg/m^2. Patients who experience grade 3 or 4 stomatitis should have their Docetaxel Injection dose decreased to 60 mg/m^2. Patients who experience severe or cumulative cutaneous reactions or moderate neurosensory signs and/or symptoms during Docetaxel Injection therapy should have their dosage of Docetaxel Injection reduced from 75 mg/m^2 to 60 mg/m^2. If the patient continues to experience these reactions at 60 mg/m^2, treatment should be discontinued.

Non-small Cell Lung Cancer

Monotherapy with Docetaxel Injection for NSCLC Treatment after Failure of Prior Platinum-Based Chemotherapy

Patients who are dosed initially at 75 mg/m^2 and who experience either febrile neutropenia, neutrophils <500 cells/mm^3 for more than one week, severe or cumulative cutaneous reactions, or other grade 3/4 non-hematological toxicities during Docetaxel Injection treatment should have treatment withheld until resolution of the toxicity and then resumed at 55 mg/m^2. Patients who develop ≥grade 3 peripheral neuropathy should have Docetaxel Injection treatment discontinued entirely.

Combination Therapy with Docetaxel Injection for Chemotherapy-Naïve NSCLC

For patients who are dosed initially at Docetaxel Injection 75 mg/m^2 in combination with cisplatin, and whose nadir of platelet count during the previous course of therapy is <25,000 cells/mm^3, in patients who experience febrile neutropenia, and in patients with serious non-hematologic toxicities, the Docetaxel Injection dosage in subsequent cycles should be reduced to 65 mg/m^2. In patients who require a further dose reduction, a dose of 50 mg/m^2 is recommended. For cisplatin dosage adjustments, see manufacturers' prescribing information.

Prostate Cancer

Combination Therapy with Docetaxel Injection for Metastatic Castration-Resistant Prostate Cancer

Docetaxel Injection should be administered when the neutrophil count is ≥1500 cells/mm^3. Patients who experience either febrile neutropenia, neutrophils <500 cells/mm^3 for more than one week, severe or cumulative cutaneous reactions or moderate neurosensory signs and/or symptoms during Docetaxel Injection therapy should have the dosage of Docetaxel Injection reduced from 75 mg/m^2 to 60 mg/m^2. If the patient continues to experience these reactions at 60 mg/m^2, the treatment should be discontinued.

Gastric or Head and Neck Cancer

Docetaxel Injection in Combination with Cisplatin and Fluorouracil in Gastric Cancer or Head and Neck Cancer

Patients treated with Docetaxel Injection in combination with cisplatin and fluorouracil must receive antiemetics and appropriate hydration according to current institutional guidelines. In both studies, G-CSF was recommended during the second and/or subsequent cycles in case of febrile neutropenia, or documented infection with neutropenia, or neutropenia lasting more than 7 days. If an episode of febrile neutropenia, prolonged neutropenia or neutropenic infection occurs despite G-CSF use, the Docetaxel Injection dose should be reduced from 75 mg/m^2 to 60 mg/m^2. If subsequent episodes of complicated neutropenia occur the Docetaxel Injection dose should be reduced from 60 mg/m^2 to 45 mg/m^2. In case of grade 4 thrombocytopenia the Docetaxel Injection dose should be reduced from 75 mg/m^2 to 60 mg/m^2. Do not retreat patients with subsequent cycles of Docetaxel Injection until neutrophils recover to a level >1500 cells/mm^3 [see Contraindications (4)]. Avoid retreating patients until platelets recover to a level >100,000 cells/mm^3. Discontinue treatment if these toxicities persist [see Warnings and Precautions (5.3)].

Recommended dose modifications for toxicities in patients treated with Docetaxel Injection in combination with cisplatin and fluorouracil are shown in Table 1.

Table 1: Recommended Dose Modifications for Toxicities in Patients Treated with Docetaxel Injection in Combination with Cisplatin and Fluorouracil
Toxicity | Dosage Adjustment
Diarrhea grade 3 | First episode: reduce fluorouracil dose by 20%. Second episode: then reduce Docetaxel Injection dose by 20%.
Diarrhea grade 4 | First episode: reduce Docetaxel Injection and fluorouracil doses by 20%. Second episode: discontinue treatment.
Stomatitis/mucositis grade 3 | First episode: reduce fluorouracil dose by 20%. Second episode: stop fluorouracil only, at all subsequent cycles. Third episode: reduce Docetaxel Injection dose by 20%.
Stomatitis/mucositis grade 4 | First episode: stop fluorouracil only, at all subsequent cycles. Second episode: reduce Docetaxel Injection dose by 20%.

Liver dysfunction: In case of AST/ALT >2.5 to ≤5 × ULN and AP ≤2.5 × ULN, or AST/ALT >1.5 to ≤5 × ULN and AP >2.5 to ≤5 × ULN, Docetaxel Injection should be reduced by 20%.

In case of AST/ALT >5 × ULN and/or AP >5 × ULN Docetaxel Injection should be stopped.

The dose modifications for cisplatin and fluorouracil in the gastric cancer study are provided below.

Cisplatin Dose Modifications and Delays

Peripheral Neuropathy: A neurological examination should be performed before entry into the study, and then at least every 2 cycles and at the end of treatment. In the case of neurological signs or symptoms, more frequent examinations should be performed and the following dose modifications can be made according to NCI-CTCAE grade:

- Grade 2: Reduce cisplatin dose by 20%.
- Grade 3: Discontinue treatment.

Ototoxicity: In the case of grade 3 toxicity, discontinue treatment.

Nephrotoxicity: In the event of a rise in serum creatinine ≥grade 2 (>1.5 × normal value) despite adequate rehydration, CrCl should be determined before each subsequent cycle and the following dose reductions should be considered (see Table 2).

For other cisplatin dosage adjustments, also refer to the manufacturers' prescribing information.

Table 2: Dose Reductions for Evaluation of Creatinine Clearance
Creatinine Clearance Result Before Next Cycle | Cisplatin Dose Next Cycle
CrCl ≥60 mL/min | Full dose of cisplatin was given. CrCl was to be repeated before each treatment cycle.
CrCl between 40 and 59 mL/min | Dose of cisplatin was reduced by 50% at subsequent cycle. If CrCl was >60 mL/min at end of cycle, full cisplatin dose was reinstituted at the next cycle. If no recovery was observed, then cisplatin was omitted from the next treatment cycle.
CrCl <40 mL/min | Dose of cisplatin was omitted in that treatment cycle only. If CrCl was still <40 mL/min at the end of cycle, cisplatin was discontinued. If CrCl was >40 and <60 mL/min at end of cycle, a 50% cisplatin dose was given at the next cycle. If CrCl was >60 mL/min at end of cycle, full cisplatin dose was given at next cycle.
CrCl = Creatinine clearance

Fluorouracil Dose Modifications and Treatment Delays

For diarrhea and stomatitis, see Table 1.

In the event of grade 2 or greater plantar-palmar toxicity, fluorouracil should be stopped until recovery. The fluorouracil dosage should be reduced by 20%.

For other greater than grade 3 toxicities, except alopecia and anemia, chemotherapy should be delayed (for a maximum of 2 weeks from the planned date of infusion) until resolution to grade ≤1 and then recommenced, if medically appropriate.

For other fluorouracil dosage adjustments, also refer to the manufacturers' prescribing information.

Combination Therapy with Strong CYP3A4 Inhibitors

Avoid using concomitant strong CYP3A4 inhibitors (e.g., ketoconazole, itraconazole, clarithromycin, atazanavir, indinavir, nefazodone, nelfinavir, ritonavir, saquinavir, telithromycin and voriconazole). There are no clinical data with a dose adjustment in patients receiving strong CYP3A4 inhibitors. Based on extrapolation from a pharmacokinetic study with ketoconazole in 7 patients, consider a 50% docetaxel dose reduction if patients require coadministration of a strong CYP3A4 inhibitor [see Drug Interactions (7), Clinical Pharmacology (12.3)].

2.8 Administration Precautions

Docetaxel Injection is a hazardous anticancer drug and, as with other potentially toxic compounds, caution should be exercised when handling and preparing Docetaxel Injection solutions. The use of gloves is recommended [see How Supplied/Storage and Handling (16.3)].

If Docetaxel Injection or final dilution for infusion should come into contact with the skin, immediately and thoroughly wash with soap and water. If Docetaxel Injection or final dilution for infusion should come into contact with mucosa, immediately and thoroughly wash with water.

Contact of the Docetaxel Injection with plasticized PVC equipment or devices used to prepare solutions for infusion is not recommended. In order to minimize patient exposure to the plasticizer DEHP (di-2-ethylhexyl phthalate), which may be leached from PVC infusion bags or sets, the final Docetaxel Injection dilution for infusion should be stored in bottles (glass, polypropylene) or plastic bags (polypropylene, polyolefin) and administered through polyethylene-lined administration sets.

Docetaxel Injection requires NO prior dilution with a diluent and is ready to add to the infusion solution.

Please follow the preparation instructions provided below.

2.9 Preparation and Administration

Docetaxel Injection (20 mg/mL) requires NO prior dilution with a diluent and is ready to add to the infusion solution. Use only a 21 gauge needle to withdraw Docetaxel Injection from the vial because larger bore needles (e.g., 18 and 19 gauge) may result in stopper coring and rubber particulates.

Dilution for Infusion

1. Docetaxel Injection vials should be stored between 2°C and 25°C (36°F and 77°F). If the vials are stored under refrigeration, allow the appropriate number of vials of Docetaxel Injection vials to stand at room temperature for approximately 5 minutes before use.
2. Using only a 21 gauge needle, aseptically withdraw the required amount of Docetaxel Injection (20 mg docetaxel/mL) with a calibrated syringe and inject via a single injection (one shot) into a 250 mL infusion bag or bottle of either 0.9% Sodium Chloride solution or 5% Dextrose solution to produce a final concentration of 0.3 mg/mL to 0.74 mg/mL.
  If a dose greater than 200 mg of docetaxel is required, use a larger volume of the infusion vehicle so that a concentration of 0.74 mg/mL docetaxel is not exceeded.
3. Thoroughly mix the infusion by gentle manual rotation.
4. As with all parenteral products, Docetaxel Injection should be inspected visually for particulate matter or discoloration prior to administration whenever the solution and container permit. If the Docetaxel Injection dilution for intravenous infusion is not clear or appears to have precipitation, it should be discarded.
5. Docetaxel Injection infusion solution is supersaturated, therefore may crystallize over time. If crystals appear, the solution must no longer be used and shall be discarded.

The Docetaxel Injection dilution for infusion should be administered intravenously as a 1-hour infusion under ambient room temperature (below 25°C) and lighting conditions.

2.10 Stability

Docetaxel Injection final dilution for infusion, if stored between 2°C and 25°C (36°F and 77°F), is stable for 6 hours. Docetaxel Injection final dilution for infusion (in either 0.9% Sodium Chloride solution or 5% Dextrose solution) should be used within 6 hours (including the 1 hour intravenous administration).

In addition, physical and chemical in-use stability of the infusion solution prepared as recommended has been demonstrated in non-PVC bags up to 48 hours when stored between 2°C and 8°C (36°F and 46°F).

3 DOSAGE FORMS AND STRENGTHS

Docetaxel Injection, USP is a pale-yellow to brownish yellow solution available as:

- 20 mg/mL single-dose vial
- 80 mg/4 mL (20 mg/mL) multiple-dose vial
- 160 mg/8 mL (20 mg/mL) multiple-dose vial

4 CONTRAINDICATIONS

Docetaxel Injection is contraindicated in patients with:

- neutrophil counts of <1500 cells/mm^3 [see Warnings and Precautions (5.3)].
- a history of severe hypersensitivity reactions to docetaxel or to other drugs formulated with polysorbate 80. Severe reactions, including anaphylaxis, have occurred [see Warnings and Precautions (5.5)].

5 WARNINGS AND PRECAUTIONS

5.1 Toxic Deaths

Breast Cancer

Docetaxel administered at 100 mg/m^2 was associated with deaths considered possibly or probably related to treatment in 2.0% (19/965) of metastatic breast cancer patients, both previously treated and untreated, with normal baseline liver function and in 11.5% (7/61) of patients with various tumor types who had abnormal baseline liver function (AST and/or ALT >1.5 times ULN together with AP >2.5 times ULN). Among patients dosed at 60 mg/m^2, mortality related to treatment occurred in 0.6% (3/481) of patients with normal liver function, and in 3 of 7 patients with abnormal liver function. Approximately half of these deaths occurred during the first cycle. Sepsis accounted for the majority of the deaths.

Non-small Cell Lung Cancer

Docetaxel administered at a dose of 100 mg/m^2 in patients with locally advanced or metastatic non-small cell lung cancer who had a history of prior platinum-based chemotherapy was associated with increased treatment-related mortality (14% and 5% in two randomized, controlled studies). There were 2.8% treatment-related deaths among the 176 patients treated at the 75 mg/m^2 dose in the randomized trials. Among patients who experienced treatment-related mortality at the 75 mg/m^2 dose level, 3 of 5 patients had an ECOG PS of 2 at study entry [see Dosage and Administration (2.2), Clinical Studies (14)].

5.2 Hepatic Impairment

Patients with elevations of bilirubin or abnormalities of transaminase concurrent with alkaline phosphatase are at increased risk for the development of severe neutropenia, febrile neutropenia, infections, severe thrombocytopenia, severe stomatitis, severe skin toxicity, and toxic death.

Avoid Docetaxel Injection in patients with bilirubin > upper limit of normal (ULN), or to patients with AST and/or ALT >1.5 × ULN concomitant with alkaline phosphatase >2.5 × ULN [see Warnings and Precautions (5.1)].

For patients with isolated elevations of transaminase >1.5 × ULN, consider Docetaxel Injection dose modifications [see Dosage and Administration (2.7)].

Measure bilirubin, AST or ALT, and alkaline phosphatase prior to each cycle of Docetaxel Injection therapy.

5.3 Hematologic Effects

Perform frequent peripheral blood cell counts on all patients receiving Docetaxel Injection. Do not retreat patients with subsequent cycles of Docetaxel Injection until neutrophils recover to a level >1500 cells/mm^3 [see Contraindications (4)]. Avoid retreating patients until platelets recover to a level >100,000 cells/mm^3.

A 25% reduction in the dose of Docetaxel Injection is recommended during subsequent cycles following severe neutropenia (<500 cells/mm^3) lasting 7 days or more, febrile neutropenia, or a grade 4 infection in a Docetaxel Injection cycle [see Dosage and Administration (2.7)].

Neutropenia (<2000 neutrophils/mm^3) occurs in virtually all patients given 60 mg/m^2 to 100 mg/m^2 of docetaxel and grade 4 neutropenia (<500 cells/mm^3) occurs in 85% of patients given 100 mg/m^2 and 75% of patients given 60 mg/m^2. Frequent monitoring of blood counts is, therefore, essential so that dose can be adjusted. Docetaxel Injection should not be administered to patients with neutrophils <1500 cells/mm^3.

Febrile neutropenia occurred in about 12% of patients given 100 mg/m^2 but was very uncommon in patients given 60 mg/m^2.

Hematologic responses, febrile reactions and infections, and rates of septic death for different regimens are dose related [see Adverse Reactions (6.1), Clinical Studies (14)].

Three breast cancer patients with severe liver impairment (bilirubin >1.7 times ULN) developed fatal gastrointestinal bleeding associated with severe drug-induced thrombocytopenia. In gastric cancer patients treated with docetaxel in combination with cisplatin and fluorouracil (TCF), febrile neutropenia and/or neutropenic infection occurred in 12% of patients receiving G-CSF compared to 28% who did not. Patients receiving TCF should be closely monitored during the first and subsequent cycles for febrile neutropenia and neutropenic infection [see Dosage and Administration (2.7), Adverse Reactions (6)].

5.4 Enterocolitis and Neutropenic Colitis

Enterocolitis and neutropenic colitis (typhlitis) have occurred in patients treated with Docetaxel Injection alone and in combination with other chemotherapeutic agents, despite the coadministration of G-CSF. Caution is recommended for patients with neutropenia, particularly at risk for developing gastrointestinal complications. Enterocolitis and neutropenic enterocolitis may develop at any time, and could lead to death as early as the first day of symptom onset.

Monitor patients closely from onset of any symptoms of gastrointestinal toxicity. Inform patients to contact their healthcare provider with new, or worsening symptoms of gastrointestinal toxicity [see Dosage and Administration (2), Warnings and Precautions (5.3), Adverse Reactions (6.2)].

5.5 Hypersensitivity Reactions

Monitor patients closely for hypersensitivity reactions, especially during the first and second infusions. Severe hypersensitivity reactions characterized by generalized rash/erythema, hypotension and/or bronchospasm, or fatal anaphylaxis, have been reported in patients premedicated with 3 days of corticosteroids. Severe hypersensitivity reactions require immediate discontinuation of the Docetaxel Injection infusion and aggressive therapy. Do not rechallenge patients with a history of severe hypersensitivity reactions with Docetaxel Injection [see Contraindications (4)].

Patients who have previously experienced a hypersensitivity reaction to paclitaxel may develop a hypersensitivity reaction to docetaxel that may include severe or fatal reactions such as anaphylaxis. Monitor patients with a previous history of hypersensitivity to paclitaxel closely during initiation of docetaxel therapy. Hypersensitivity reactions may occur within a few minutes following initiation of a Docetaxel Injection infusion. If minor reactions such as flushing or localized skin reactions occur, interruption of therapy is not required. All patients should be premedicated with an oral corticosteroid prior to the initiation of the infusion of Docetaxel Injection [see Dosage and Administration (2.6)].

5.6 Fluid Retention

Severe fluid retention has been reported following docetaxel therapy. Patients should be premedicated with oral corticosteroids prior to each Docetaxel Injection administration to reduce the incidence and severity of fluid retention [see Dosage and Administration (2.6)]. Patients with pre-existing effusions should be closely monitored from the first dose for the possible exacerbation of the effusions.

When fluid retention occurs, peripheral edema usually starts in the lower extremities and may become generalized with a median weight gain of 2 kg.

Among 92 breast cancer patients premedicated with 3-day corticosteroids, moderate fluid retention occurred in 27.2% and severe fluid retention in 6.5%. The median cumulative dose to onset of moderate or severe fluid retention was 819 mg/m^2. Nine of 92 patients (9.8%) of patients discontinued treatment due to fluid retention: 4 patients discontinued with severe fluid retention; the remaining 5 had mild or moderate fluid retention. The median cumulative dose to treatment discontinuation due to fluid retention was 1021 mg/m^2. Fluid retention was completely, but sometimes slowly, reversible with a median of 16 weeks from the last infusion of docetaxel to resolution (range: 0 to 42+ weeks). Patients developing peripheral edema may be treated with standard measures, e.g., salt restriction, oral diuretic(s).

5.7 Second Primary Malignancies

Second primary malignancies, notably acute myeloid leukemia (AML), myelodysplastic syndrome (MDS), Non-Hodgkin's Lymphoma (NHL), and renal cancer, have been reported in patients treated with docetaxel-containing regimens. These adverse reactions may occur several months or years after docetaxel-containing therapy.

Treatment-related AML or MDS has occurred in patients given anthracyclines and/or cyclophosphamide, including use in adjuvant therapy for breast cancer. In the adjuvant breast cancer trial (TAX316) AML occurred in 3 of 744 patients who received docetaxel, doxorubicin, and cyclophosphamide (TAC) and in 1 of 736 patients who received fluorouracil, doxorubicin, and cyclophosphamide [see Clinical Studies (14.2)]. In TAC-treated patients, the risk of delayed myelodysplasia or myeloid leukemia requires hematological follow-up. Monitor patients for second primary malignancies [see Adverse Reactions (6.1)].

5.8 Cutaneous Reactions

Localized erythema of the extremities with edema followed by desquamation has been observed. In case of severe skin toxicity, an adjustment in dosage is recommended [see Dosage and Administration (2.7)]. The discontinuation rate due to skin toxicity was 1.6% (15/965) for metastatic breast cancer patients. Among 92 breast cancer patients premedicated with 3-day corticosteroids, there were no cases of severe skin toxicity reported and no patient discontinued docetaxel due to skin toxicity.

Severe cutaneous adverse reactions (SCARs) such as Stevens-Johnson syndrome (SJS), toxic epidermal necrolysis (TEN), and acute generalized exanthematous pustulosis (AGEP) have been reported in association with docetaxel treatment. Patients should be informed about the signs and symptoms of serious skin manifestations and monitored closely. Permanent treatment discontinuation should be considered in patients who experience SCARs.

5.9 Neurologic Reactions

Severe neurosensory symptoms (e.g., paresthesia, dysesthesia, pain) were observed in 5.5% (53/965) of metastatic breast cancer patients, and resulted in treatment discontinuation in 6.1%. When these symptoms occur, dosage must be adjusted. If symptoms persist, treatment should be discontinued [see Dosage and Administration (2.7)]. Patients who experienced neurotoxicity in clinical trials and for whom follow-up information on the complete resolution of the event was available had spontaneous reversal of symptoms with a median of 9 weeks from onset (range: 0 to 106 weeks). Severe peripheral motor neuropathy mainly manifested as distal extremity weakness occurred in 4.4% (42/965).

5.10 Eye Disorders

Cystoid macular edema (CME) has been reported in patients treated with Docetaxel Injection. Patients with impaired vision should undergo a prompt and comprehensive ophthalmologic examination. If CME is diagnosed, Docetaxel Injection treatment should be discontinued and appropriate treatment initiated. Alternative non-taxane cancer treatment should be considered.

5.11 Asthenia

Severe asthenia has been reported in 14.9% (144/965) of metastatic breast cancer patients but has led to treatment discontinuation in only 1.8%. Symptoms of fatigue and weakness may last a few days up to several weeks and may be associated with deterioration of performance status in patients with progressive disease.

5.12 Embryo-Fetal Toxicity

Based on findings from animal reproduction studies and its mechanism of action, Docetaxel Injection can cause fetal harm when administered to a pregnant woman [see Clinical Pharmacology (12.1)]. Available data from case reports in the literature and pharmacovigilance with docetaxel use in pregnant women are not sufficient to inform the drug-associated risk of major birth defects, miscarriage or adverse maternal or fetal outcomes. In animal reproduction studies, administration of docetaxel to pregnant rats and rabbits during the period of organogenesis caused embryo-fetal toxicities, including intrauterine mortality, at doses as low as 0.02 and 0.003 times the recommended human dose based on body surface area, respectively.

Advise pregnant women and females of reproductive potential of the potential risk to a fetus. Verify pregnancy status in females of reproductive potential prior to initiating Docetaxel Injection. Advise females of reproductive potential to use effective contraception during treatment and for 2 months after the last dose of Docetaxel Injection. Advise male patients with female partners of reproductive potential to use effective contraception during treatment and for 4 months after the last dose of Docetaxel Injection [see Use in Specific Populations (8.1, 8.3)].

5.13 Alcohol Content

Cases of intoxication have been reported with some formulations of docetaxel due to the alcohol content. The alcohol content in a dose of Docetaxel Injection may affect the central nervous system and should be taken into account for patients in whom alcohol intake should be avoided or minimized. Consideration should be given to the alcohol content in Docetaxel Injection on the ability to drive or use machines immediately after the infusion. Each administration of Docetaxel Injection at 100 mg/m^2 delivers 2.0 g/m^2 of ethanol. For a patient with a BSA of 2.0 m^2, this would deliver 4.0 grams of ethanol [see Description (11)]. Other docetaxel products may have a different amount of alcohol.

5.14 Tumor Lysis Syndrome

Tumor lysis syndrome has been reported with docetaxel [see Adverse Reactions (6.2)]. Patients at risk of tumor lysis syndrome (e.g., with renal impairment, hyperuricemia, bulky tumor) should be closely monitored prior to initiating Docetaxel Injection and periodically during treatment. Correction of dehydration and treatment of high uric acid levels are recommended prior to initiation of treatment.

6 ADVERSE REACTIONS

The most serious adverse reactions from docetaxel are:

- Toxic Deaths [see Boxed Warning, Warnings and Precautions (5.1)]
- Hepatic Impairment [see Boxed Warning, Warnings and Precautions (5.2)]
- Hematologic Effects [see Boxed Warning, Warnings and Precautions (5.3)]
- Enterocolitis and Neutropenic Colitis [see Warnings and Precautions (5.4)]
- Hypersensitivity Reactions [see Boxed Warning, Warnings and Precautions (5.5)]
- Fluid Retention [see Boxed Warning, Warnings and Precautions (5.6)]
- Second Primary Malignancies [see Warnings and Precautions (5.7)]
- Cutaneous Reactions [see Warnings and Precautions (5.8)]
- Neurologic Reactions [see Warnings and Precautions (5.9)]
- Eye Disorders [see Warnings and Precautions (5.10)]
- Asthenia [see Warnings and Precautions (5.11)]
- Alcohol Content [see Warnings and Precautions (5.13)]

The most common adverse reactions across all docetaxel indications are infections, neutropenia, anemia, febrile neutropenia, hypersensitivity, thrombocytopenia, neuropathy, dysgeusia, dyspnea, constipation, anorexia, nail disorders, fluid retention, asthenia, pain, nausea, diarrhea, vomiting, mucositis, alopecia, skin reactions, and myalgia. Incidence varies depending on the indication.

Adverse reactions are described according to indication. Because clinical trials are conducted under widely varying conditions, adverse reaction rates observed in the clinical trials of a drug cannot be directly compared to rates in the clinical trials of another drug and may not reflect the rates observed in practice.

Responding patients may not experience an improvement in performance status on therapy and may experience worsening. The relationship between changes in performance status, response to therapy, and treatment-related side effects has not been established.

6.1 Clinical Trials Experience

Breast Cancer

Monotherapy with Docetaxel for Locally Advanced or Metastatic Breast Cancer after Failure of Prior Chemotherapy

Docetaxel 100 mg/m^2: Adverse drug reactions occurring in at least 5% of patients are compared for three populations who received docetaxel administered at 100 mg/m^2 as a 1-hour infusion every 3 weeks: 2045 patients with various tumor types and normal baseline liver function tests; the subset of 965 patients with locally advanced or metastatic breast cancer, both previously treated and untreated with chemotherapy, who had normal baseline liver function tests; and an additional 61 patients with various tumor types who had abnormal liver function tests at baseline. These reactions were described using COSTART terms and were considered possibly or probably related to docetaxel. At least 95% of these patients did not receive hematopoietic support. The safety profile is generally similar in patients receiving docetaxel for the treatment of breast cancer and in patients with other tumor types (see Table 3).

Table 3: Summary of Adverse Reactions in Patients Receiving Docetaxel at 100 mg/m^2
Adverse Reaction | All Tumor Types Normal LFTs [Normal Baseline LFTs: Transaminases ≤1.5 times ULN or alkaline phosphatase ≤2.5 times ULN or isolated elevations of transaminases or alkaline phosphatase up to 5 times ULN] n=2045 % | All Tumor Types Elevated LFTs [Elevated Baseline LFTs: AST and/or ALT >1.5 times ULN concurrent with alkaline phosphatase >2.5 times ULN] n=61 % | Breast Cancer Normal LFTs n=965 %
Hematologic
Neutropenia
<2000 cells/mm^3 | 96 | 96 | 99
<500 cells/mm^3 | 75 | 88 | 86
Leukopenia
<4000 cells/mm^3 | 96 | 98 | 99
<1000 cells/mm^3 | 32 | 47 | 44
Thrombocytopenia
<100,000 cells/mm^3 | 8 | 25 | 9
Anemia
<11 g/dL | 90 | 92 | 94
<8 g/dL | 9 | 31 | 8
Febrile Neutropenia [Febrile Neutropenia: ANC grade 4 with fever >38°C with intravenous antibiotics and/or hospitalization] | 11 | 26 | 12
Septic Death | 2 | 5 | 1
Non-Septic Death | 1 | 7 | 1
Infections
Any | 22 | 33 | 22
Severe | 6 | 16 | 6
Fever in Absence of Infection
Any | 31 | 41 | 35
Severe | 2 | 8 | 2
Hypersensitivity Reactions
Regardless of Premedication
Any | 21 | 20 | 18
Severe | 4 | 10 | 3
With 3-day Premedication | n=92 | n=3 | n=92
Any | 15 | 33 | 15
Severe | 2 | 0 | 2
Fluid Retention
Regardless of Premedication
Any | 47 | 39 | 60
Severe | 7 | 8 | 9
With 3-day Premedication | n=92 | n=3 | n=92
Any | 64 | 67 | 64
Severe | 7 | 33 | 7
Neurosensory
Any | 49 | 34 | 58
Severe | 4 | 0 | 6
Cutaneous
Any | 48 | 54 | 47
Severe | 5 | 10 | 5
Nail Changes
Any | 31 | 23 | 41
Severe | 3 | 5 | 4
Gastrointestinal
Nausea | 39 | 38 | 42
Vomiting | 22 | 23 | 23
Diarrhea | 39 | 33 | 43
Severe | 5 | 5 | 6
Stomatitis
Any | 42 | 49 | 52
Severe | 6 | 13 | 7
Alopecia | 76 | 62 | 74
Asthenia
Any | 62 | 53 | 66
Severe | 13 | 25 | 15
Myalgia
Any | 19 | 16 | 21
Severe | 2 | 2 | 2
Arthralgia | 9 | 7 | 8
Infusion Site Reactions | 4 | 3 | 4

Hematologic Reactions

Reversible marrow suppression was the major dose-limiting toxicity of docetaxel [see Warnings and Precautions (5.3)]. The median time to nadir was 7 days, while the median duration of severe neutropenia (<500 cells/mm^3) was 7 days. Among 2045 patients with solid tumors and normal baseline LFTs, severe neutropenia occurred in 75.4% and lasted for more than 7 days in 2.9% of cycles.

Febrile neutropenia (<500 cells/mm^3 with fever >38°C with intravenous antibiotics and/or hospitalization) occurred in 11% of patients with solid tumors, in 12.3% of patients with metastatic breast cancer, and in 9.8% of 92 breast cancer patients premedicated with 3-day corticosteroids.

Severe infectious episodes occurred in 6.1% of patients with solid tumors, in 6.4% of patients with metastatic breast cancer, and in 5.4% of 92 breast cancer patients premedicated with 3-day corticosteroids.

Thrombocytopenia (<100,000 cells/mm^3) associated with fatal gastrointestinal hemorrhage has been reported.

Hypersensitivity Reactions

Severe hypersensitivity reactions have been reported [see Boxed Warning, Warnings and Precautions (5.5)]. Minor events, including flushing, rash with or without pruritus, chest tightness, back pain, dyspnea, drug fever, or chills, have been reported and resolved after discontinuing the infusion and instituting appropriate therapy.

Fluid Retention

Fluid retention can occur with the use of docetaxel [see Boxed Warning, Dosage and Administration (2.6), Warnings and Precautions (5.6)].

Cutaneous Reactions

Severe skin toxicity is discussed elsewhere in the label [see Warnings and Precautions (5.8)]. Reversible cutaneous reactions characterized by a rash including localized eruptions, mainly on the feet and/or hands, but also on the arms, face, or thorax, usually associated with pruritus, have been observed. Eruptions generally occurred within 1 week after docetaxel infusion, recovered before the next infusion, and were not disabling.

Severe nail disorders were characterized by hypo- or hyperpigmentation, and occasionally by onycholysis (in 0.8% of patients with solid tumors) and pain.

Neurologic Reactions

Neurologic reactions are discussed elsewhere in the label [see Warnings and Precautions (5.9)].

Gastrointestinal Reactions

Nausea, vomiting, and diarrhea were generally mild to moderate. Severe reactions occurred in 3%–5% of patients with solid tumors and to a similar extent among metastatic breast cancer patients. The incidence of severe reactions was 1% or less for the 92 breast cancer patients premedicated with 3-day corticosteroids.

Severe stomatitis occurred in 5.5% of patients with solid tumors, in 7.4% of patients with metastatic breast cancer, and in 1.1% of the 92 breast cancer patients premedicated with 3-day corticosteroids.

Cardiovascular Reactions

Hypotension occurred in 2.8% of patients with solid tumors; 1.2% required treatment. Clinically meaningful events such as heart failure, sinus tachycardia, atrial flutter, dysrhythmia, unstable angina, pulmonary edema, and hypertension have occurred. Seven of 86 (8.1%) of metastatic breast cancer patients receiving docetaxel 100 mg/m^2 in a randomized trial and who had serial left ventricular ejection fractions assessed developed deterioration of LVEF by ≥10% associated with a drop below the institutional lower limit of normal.

Infusion Site Reactions

Infusion site reactions were generally mild and consisted of hyperpigmentation, inflammation, redness or dryness of the skin, phlebitis, extravasation, or swelling of the vein.

Hepatic Reactions

In patients with normal LFTs at baseline, bilirubin values greater than the ULN occurred in 8.9% of patients. Increases in AST or ALT >1.5 times the ULN, or alkaline phosphatase >2.5 times ULN, were observed in 18.9% and 7.3% of patients, respectively. While on docetaxel, increases in AST and/or ALT >1.5 times ULN concomitant with alkaline phosphatase >2.5 times ULN occurred in 4.3% of patients with normal LFTs at baseline. Whether these changes were related to the drug or underlying disease has not been established.

Hematologic and Other Toxicity: Relation to Dose and Baseline Liver Chemistry Abnormalities

Hematologic and other toxicity is increased at higher doses and in patients with elevated baseline liver function tests (LFTs). In the following tables, adverse drug reactions are compared for three populations: 730 patients with normal LFTs given docetaxel at 100 mg/m^2 in the randomized and single arm studies of metastatic breast cancer after failure of previous chemotherapy; 18 patients in these studies who had abnormal baseline LFTs (defined as AST and/or ALT >1.5 times ULN concurrent with alkaline phosphatase >2.5 times ULN); and 174 patients in Japanese studies given docetaxel at 60 mg/m^2 who had normal LFTs (see Tables 4 and 5).

Table 4: Hematologic Adverse Reactions in Breast Cancer Patients Previously Treated with Chemotherapy Treated at Docetaxel 100 mg/m^2 with Normal or Elevated Liver Function Tests or 60 mg/m^2 with Normal Liver Function Tests
Adverse Reaction | Docetaxel; 100 mg/m^2 |  | Docetaxel; 60mg/m^2
Adverse Reaction | Normal LFTs [Normal Baseline LFTs: Transaminases ≤1.5 times ULN or alkaline phosphatase ≤2.5 times ULN or isolated elevations of transaminases or alkaline phosphatase up to 5 times ULN] n=730 % | Elevated LFTs [Elevated Baseline LFTs: AST and/or ALT >1.5 times ULN concurrent with alkaline phosphatase >2.5 times ULN] n=18 % | Normal LFTs n=174 %
Neutropenia
Any <2000 cells/mm^3 | 98 | 100 | 95
Grade 4 <500 cells/mm^3 | 84 | 94 | 75
Thrombocytopenia
Any <100,000 cells/mm^3 | 11 | 44 | 14
Grade 4 <20,000 cells/mm^3 | 1 | 17 | 1
Anemia <11 g/dL | 95 | 94 | 65
Infection [Incidence of infection requiring hospitalization and/or intravenous antibiotics was 8.5% (n=62) among the 730 patients with normal LFTs at baseline; 7 patients had concurrent grade 3 neutropenia, and 46 patients had grade 4 neutropenia.]
Any | 23 | 39 | 1
Grade 3 and 4 | 7 | 33 | 0
Febrile Neutropenia [Febrile Neutropenia: For 100 mg/m^2, ANC grade 4 and fever >38°C with intravenous antibiotics and/or hospitalization; for 60 mg/m^2, ANC grade 3/4 and fever >38.1°C]
By Patient | 12 | 33 | 0
By Course | 2 | 9 | 0
Septic Death | 2 | 6 | 1
Non-Septic Death | 1 | 11 | 0

Table 5: Non-Hematologic Adverse Reactions in Breast Cancer Patients Previously Treated with Chemotherapy Treated at Docetaxel 100 mg/m^2 with Normal or Elevated Liver Function Tests or 60 mg/m^2 with Normal Liver Function Tests
Adverse Reaction | Docetaxel; 100 mg/m^2 |  | Docetaxel; 60 mg/m^2
Adverse Reaction | Normal LFTs [Normal Baseline LFTs: Transaminases ≤1.5 times ULN or alkaline phosphatase ≤2.5 times ULN or isolated elevations of transaminases or alkaline phosphatase up to 5 times ULN] n=730 % | Elevated LFTs [Elevated Baseline Liver Function: AST and/or ALT >1.5 times ULN concurrent with alkaline phosphatase >2.5 times ULN] n=18 % | Normal LFTs n=174 %
Acute Hypersensitivity Reaction
Regardless of Premedication
Any | 13 | 6 | 1
Severe | 1 | 0 | 0
Fluid Retention [Fluid Retention includes (by COSTART): edema (peripheral, localized, generalized, lymphedema, pulmonary edema, and edema otherwise not specified) and effusion (pleural, pericardial, and ascites); no premedication given with the 60 mg/m^2 dose]
Regardless of Premedication
Any | 56 | 61 | 13
Severe | 8 | 17 | 0
Neurosensory
Any | 57 | 50 | 20
Severe | 6 | 0 | 0
Myalgia | 23 | 33 | 3
Cutaneous
Any | 45 | 61 | 31
Severe | 5 | 17 | 0
Asthenia
Any | 65 | 44 | 66
Severe | 17 | 22 | 0
Diarrhea
Any | 42 | 28 | NA
Severe | 6 | 11
Stomatitis
Any | 53 | 67 | 19
Severe | 8 | 39 | 1
NA = not available

In the three-arm monotherapy trial, TAX313, which compared docetaxel 60 mg/m^2, 75 mg/m^2 and 100 mg/m^2 in advanced breast cancer, grade 3/4 or severe adverse reactions occurred in 49.0% of patients treated with docetaxel 60 mg/m^2 compared to 55.3% and 65.9% treated with 75 mg/m^2 and 100 mg/m^2, respectively. Discontinuation due to adverse reactions was reported in 5.3% of patients treated with 60 mg/m^2 versus 6.9% and 16.5% for patients treated at 75 mg/m^2 and 100 mg/m^2, respectively. Deaths within 30 days of last treatment occurred in 4.0% of patients treated with 60 mg/m^2 compared to 5.3% and 1.6% for patients treated at 75 mg/m^2 and 100 mg/m^2, respectively.

The following adverse reactions were associated with increasing docetaxel doses: fluid retention (26%, 38%, and 46% at 60 mg/m^2, 75 mg/m^2, and 100 mg/m^2, respectively), thrombocytopenia (7%, 11% and 12%, respectively), neutropenia (92%, 94%, and 97%, respectively), febrile neutropenia (5%, 7%, and 14%, respectively), treatment-related grade 3/4 infection (2%, 3%, and 7%, respectively) and anemia (87%, 94%, and 97%, respectively).

Combination Therapy with Docetaxel in the Adjuvant Treatment of Breast Cancer

The following table presents treatment-emergent adverse reactions observed in 744 patients, who were treated with docetaxel 75 mg/m^2 every 3 weeks in combination with doxorubicin and cyclophosphamide (see Table 6).

Table 6: Clinically Important Treatment-Emergent Adverse Reactions Regardless of Causal Relationship in Patients Receiving Docetaxel in Combination with Doxorubicin and Cyclophosphamide (TAX316)
 | Docetaxel 75 mg/m^2 + Doxorubicin 50 mg/m^2 + Cyclophosphamide 500 mg/m^2 (TAC) n=744 % |  | Fluorouracil 500 mg/m^2 + Doxorubicin 50 mg/m^2 + Cyclophosphamide 500 mg/m^2 (FAC) n=736 %
Adverse Reaction | Any | Grade 3/4 | Any | Grade 3/4
Anemia | 92 | 4 | 72 | 2
Neutropenia | 71 | 66 | 82 | 49
Fever in absence of infection | 47 | 1 | 17 | 0
Infection | 39 | 4 | 36 | 2
Thrombocytopenia | 39 | 2 | 28 | 1
Febrile neutropenia | 25 | N/A | 3 | N/A
Neutropenic infection | 12 | N/A | 6 | N/A
Hypersensitivity reactions | 13 | 1 | 4 | 0
Lymphedema | 4 | 0 | 1 | 0
Fluid Retention [COSTART term and grading system for events related to treatment.] | 35 | 1 | 15 | 0
Peripheral edema | 27 | 0 | 7 | 0
Weight gain | 13 | 0 | 9 | 0
Neuropathy sensory | 26 | 0 | 10 | 0
Neuro-cortical | 5 | 1 | 6 | 1
Neuropathy motor | 4 | 0 | 2 | 0
Neuro-cerebellar | 2 | 0 | 2 | 0
Syncope | 2 | 1 | 1 | 0
Alopecia | 98 | N/A | 97 | N/A
Skin toxicity | 27 | 1 | 18 | 0
Nail disorders | 19 | 0 | 14 | 0
Nausea | 81 | 5 | 88 | 10
Stomatitis | 69 | 7 | 53 | 2
Vomiting | 45 | 4 | 59 | 7
Diarrhea | 35 | 4 | 28 | 2
Constipation | 34 | 1 | 32 | 1
Taste perversion | 28 | 1 | 15 | 0
Anorexia | 22 | 2 | 18 | 1
Abdominal Pain | 11 | 1 | 5 | 0
Amenorrhea | 62 | N/A | 52 | N/A
Cough | 14 | 0 | 10 | 0
Cardiac dysrhythmias | 8 | 0 | 6 | 0
Vasodilatation | 27 | 1 | 21 | 1
Hypotension | 2 | 0 | 1 | 0
Phlebitis | 1 | 0 | 1 | 0
Asthenia | 81 | 11 | 71 | 6
Myalgia | 27 | 1 | 10 | 0
Arthralgia | 19 | 1 | 9 | 0
Lacrimation disorder | 11 | 0 | 7 | 0
Conjunctivitis | 5 | 0 | 7 | 0

Of the 744 patients treated with TAC, 36.3% experienced severe treatment-emergent adverse reactions compared to 26.6% of the 736 patients treated with FAC. Dose reductions due to hematologic toxicity occurred in 1% of cycles in the TAC arm versus 0.1% of cycles in the FAC arm. Six percent of patients treated with TAC discontinued treatment due to adverse reactions, compared to 1.1% treated with FAC; fever in the absence of infection and allergy being the most common reasons for withdrawal among TAC-treated patients. Two patients died in each arm within 30 days of their last study treatment; 1 death per arm was attributed to study drugs.

Fever and Infection

During the treatment period, fever in the absence of infection was seen in 46.5% of TAC-treated patients and in 17.1% of FAC-treated patients. Grade 3/4 fever in the absence of infection was seen in 1.3% and 0% of TAC- and FAC-treated patients, respectively. Infection was seen in 39.4% of TAC-treated patients compared to 36.3% of FAC-treated patients. Grade 3/4 infection was seen in 3.9% and 2.2% of TAC-treated and FAC-treated patients, respectively. There were no septic deaths in either treatment arm during the treatment period.

Gastrointestinal Reactions

In addition to gastrointestinal reactions reflected in the table above, 7 patients in the TAC arm were reported to have colitis/enteritis/large intestine perforation versus one patient in the FAC arm. Five of the 7 TAC-treated patients required treatment discontinuation; no deaths due to these events occurred during the treatment period.

Cardiovascular Reactions

More cardiovascular reactions were reported in the TAC arm versus the FAC arm during the treatment period: arrhythmias, all grades (6.2% vs. 4.9%), and hypotension, all grades (1.9% vs. 0.8%). Twenty-six (26) patients (3.5%) in the TAC arm and 17 patients (2.3%) in the FAC arm developed CHF during the study period. All except one patient in each arm were diagnosed with CHF during the follow-up period. Two (2) patients in TAC arm and 4 patients in FAC arm died due to CHF. The risk of CHF was higher in the TAC arm in the first year, and then was similar in both treatment arms.

Adverse Reactions during the Follow-Up Period (Median Follow-Up Time of 8 Years)

In study TAX316, the most common adverse reactions that started during the treatment period and persisted into the follow-up period in TAC and FAC patients are described below (median follow-up time of 8 years).

Nervous System Disorders: In study TAX316, peripheral sensory neuropathy started during the treatment period and persisted into the follow-up period in 84 patients (11.3%) in TAC arm and 15 patients (2%) in FAC arm. At the end of the follow-up period (median follow-up time of 8 years), peripheral sensory neuropathy was observed to be ongoing in 10 patients (1.3%) in TAC arm, and in 2 patients (0.3%) in FAC arm.

Skin and Subcutaneous Tissue Disorders: In study TAX316, alopecia persisting into the follow-up period after the end of chemotherapy was reported in 687 of 744 TAC patients (92.3%) and 645 of 736 FAC patients (87.6%). At the end of the follow-up period (actual median follow-up time of 8 years), alopecia was observed to be ongoing in 29 TAC patients (3.9%) and 16 FAC patients (2.2%).

Reproductive System and Breast Disorders: In study TAX316, amenorrhea that started during the treatment period and persisted into the follow-up period after the end of chemotherapy was reported in 202 of 744 TAC patients (27.2%) and 125 of 736 FAC patients (17.0%). Amenorrhea was observed to be ongoing at the end of the follow-up period (median follow-up time of 8 years) in 121 of 744 TAC patients (16.3%) and 86 FAC patients (11.7%).

General Disorders and Administration Site Conditions: In study TAX316, peripheral edema that started during the treatment period and persisted into the follow-up period after the end of chemotherapy was observed in 119 of 744 TAC patients (16.0%) and 23 of 736 FAC patients (3.1%). At the end of the follow-up period (actual median follow-up time of 8 years), peripheral edema was ongoing in 19 TAC patients (2.6%) and 4 FAC patients (0.5%).

In study TAX316, lymphedema that started during the treatment period and persisted into the follow-up period after the end of chemotherapy was reported in 11 of 744 TAC patients (1.5%) and 1 of 736 FAC patients (0.1%). At the end of the follow-up period (actual median follow-up time of 8 years), lymphedema was observed to be ongoing in 6 TAC patients (0.8%) and 1 FAC patient (0.1%).

In study TAX316, asthenia that started during the treatment period and persisted into the follow-up period after the end of chemotherapy was reported in 236 of 744 TAC patients (31.7%) and 180 of 736 FAC patients (24.5%). At the end of the follow-up period (actual median follow-up time of 8 years), asthenia was observed to be ongoing in 29 TAC patients (3.9%) and 16 FAC patients (2.2%).

Acute Myeloid Leukemia (AML)/Myelodysplastic Syndrome (MDS): AML occurred in the adjuvant breast cancer trial (TAX316). The cumulative risk of developing treatment-related AML at median follow-up time of 8 years in TAX316 was 0.4% for TAC-treated patients and 0.1% for FAC-treated patients. One TAC patient (0.1%) and 1 FAC patient (0.1%) died due to AML during the follow-up period (median follow-up time of 8 years).

Myelodysplastic syndrome occurred in 2 of 744 (0.3%) patients who received TAC and in 1 of 736 (0.1%) patients who received FAC. AML occurs at a higher frequency when these agents are given in combination with radiation therapy.

Lung Cancer

Monotherapy with Docetaxel for Unresectable, Locally Advanced or Metastatic NSCLC Previously Treated with Platinum-Based Chemotherapy

Docetaxel 75 mg/m^2: Treatment-emergent adverse drug reactions are shown in Table 7. Included in this table are safety data for a total of 176 patients with non-small cell lung carcinoma and a history of prior treatment with platinum-based chemotherapy who were treated in two randomized, controlled trials. These reactions were described using NCI Common Toxicity Criteria regardless of relationship to study treatment, except for the hematologic toxicities or where otherwise noted.

Table 7: Treatment-Emergent Adverse Reactions Regardless of Relationship to Treatment in Patients Receiving Docetaxel as Monotherapy for Non-small Cell Lung Cancer Previously Treated with Platinum-Based Chemotherapy [Normal Baseline LFTs: Transaminases ≤1.5 times ULN or alkaline phosphatase ≤2.5 times ULN or isolated elevations of transaminases or alkaline phosphatase up to 5 times ULN]
Adverse Reaction | Docetaxel 75 mg/m^2 n=176 % | Best Supportive Care n=49 % | Vinorelbine/Ifosfamide n=119 %
Neutropenia
Any | 84 | 14 | 83
Grade 3/4 | 65 | 12 | 57
Leukopenia
Any | 84 | 6 | 89
Grade 3/4 | 49 | 0 | 43
Thrombocytopenia
Any | 8 | 0 | 8
Grade 3/4 | 3 | 0 | 2
Anemia
Any | 91 | 55 | 91
Grade 3/4 | 9 | 12 | 14
Febrile Neutropenia [Febrile Neutropenia: ANC grade 4 with fever >38°C with intravenous antibiotics and/or hospitalization] | 6 | NA [Not Applicable] | 1
Infection
Any | 34 | 29 | 30
Grade 3/4 | 10 | 6 | 9
Treatment Related Mortality | 3 | NA | 3
Hypersensitivity Reactions
Any | 6 | 0 | 1
Grade 3/4 | 3 | 0 | 0
Fluid Retention
Any | 34 | ND [Not Done] | 23
Severe | 3 |  | 3
Neurosensory
Any | 23 | 14 | 29
Grade 3/4 | 2 | 6 | 5
Neuromotor
Any | 16 | 8 | 10
Grade 3/4 | 5 | 6 | 3
Skin
Any | 20 | 6 | 17
Grade 3/4 | 1 | 2 | 1
Gastrointestinal
Nausea
Any | 34 | 31 | 31
Grade 3/4 | 5 | 4 | 8
Vomiting
Any | 22 | 27 | 22
Grade 3/4 | 3 | 2 | 6
Diarrhea
Any | 23 | 6 | 12
Grade 3/4 | 3 | 0 | 4
Alopecia | 56 | 35 | 50
Asthenia
Any | 53 | 57 | 54
Severe [COSTART term and grading system] | 18 | 39 | 23
Stomatitis
Any | 26 | 6 | 8
Grade 3/4 | 2 | 0 | 1
Pulmonary
Any | 41 | 49 | 45
Grade 3/4 | 21 | 29 | 19
Nail Disorder
Any | 11 | 0 | 2
Severe | 1 | 0 | 0
Myalgia
Any | 6 | 0 | 3
Severe | 0 | 0 | 0
Arthralgia
Any | 3 | 2 | 2
Severe | 0 | 0 | 1
Taste Perversion
Any | 6 | 0 | 0
Severe | 1 | 0 | 0

Combination Therapy with Docetaxel in Chemotherapy-Naïve Advanced Unresectable or Metastatic NSCLC

Table 8 presents safety data from two arms of an open label, randomized controlled trial (TAX326) that enrolled patients with unresectable stage IIIB or IV non-small cell lung cancer and no history of prior chemotherapy. Adverse reactions were described using the NCI Common Toxicity Criteria except where otherwise noted.

Table 8: Adverse Reactions Regardless of Relationship to Treatment in Chemotherapy-Naïve Advanced Non-small Cell Lung Cancer Patients Receiving Docetaxel in Combination with Cisplatin
Adverse Reaction | Docetaxel 75 mg/m^2 + Cisplatin 75 mg/m^2 n=406 % | Vinorelbine 25 mg/m^2 + Cisplatin 100 mg/m^2 n=396 %
Neutropenia
Any | 91 | 90
Grade 3/4 | 74 | 78
Febrile Neutropenia | 5 | 5
Thrombocytopenia
Any | 15 | 15
Grade 3/4 | 3 | 4
Anemia
Any | 89 | 94
Grade 3/4 | 7 | 25
Infection
Any | 35 | 37
Grade 3/4 | 8 | 8
Fever in absence of infection
Any | 33 | 29
Grade 3/4 | <1 | 1
Hypersensitivity Reaction [Replaces NCI term "Allergy"]
Any | 12 | 4
Grade 3/4 | 3 | <1
Fluid Retention [COSTART term and grading system]
Any | 54 | 42
All severe or life-threatening events | 2 | 2
Pleural effusion
Any | 23 | 22
All severe or life-threatening events | 2 | 2
Peripheral edema
Any | 34 | 18
All severe or life-threatening events | <1 | <1
Weight gain
Any | 15 | 9
All severe or life-threatening events | <1 | <1
Neurosensory
Any | 47 | 42
Grade 3/4 | 4 | 4
Neuromotor
Any | 19 | 17
Grade 3/4 | 3 | 6
Skin
Any | 16 | 14
Grade 3/4 | <1 | 1
Nausea
Any | 72 | 76
Grade 3/4 | 10 | 17
Vomiting
Any | 55 | 61
Grade 3/4 | 8 | 16
Diarrhea
Any | 47 | 25
Grade 3/4 | 7 | 3
Anorexia
Any | 42 | 40
All severe or life-threatening events | 5 | 5
Stomatitis
Any | 24 | 21
Grade 3/4 | 2 | 1
Alopecia
Any | 75 | 42
Grade 3 | <1 | 0
Asthenia
Any | 74 | 75
All severe or life-threatening events | 12 | 14
Nail Disorder
Any | 14 | <1
All severe events | <1 | 0
Myalgia
Any | 18 | 12
All severe events | <1 | <1

Deaths within 30 days of last study treatment occurred in 31 patients (7.6%) in the docetaxel+cisplatin arm and 37 patients (9.3%) in the vinorelbine+cisplatin arm. Deaths within 30 days of last study treatment attributed to study drug occurred in 9 patients (2.2%) in the docetaxel+cisplatin arm and 8 patients (2.0%) in the vinorelbine+cisplatin arm.

The second comparison in the study, vinorelbine+cisplatin versus docetaxel+carboplatin (which did not demonstrate a superior survival associated with docetaxel, [see Clinical Studies (14.3)]) demonstrated a higher incidence of thrombocytopenia, diarrhea, fluid retention, hypersensitivity reactions, skin toxicity, alopecia and nail changes on the docetaxel+carboplatin arm, while a higher incidence of anemia, neurosensory toxicity, nausea, vomiting, anorexia and asthenia was observed on the vinorelbine+cisplatin arm.

Prostate Cancer

Combination Therapy with Docetaxel in Patients with Prostate Cancer

The following data are based on the experience of 332 patients, who were treated with docetaxel 75 mg/m^2 every 3 weeks in combination with prednisone 5 mg orally twice daily (see Table 9).

Table 9: Clinically Important Treatment-Emergent Adverse Reactions (Regardless of Relationship) in Patients with Prostate Cancer who Received Docetaxel in Combination with Prednisone (TAX327)
 | Docetaxel 75 mg/m^2 every 3 weeks + prednisone 5 mg twice daily n=332 % |  | Mitoxantrone 12 mg/m^2 every 3 weeks + prednisone 5 mg twice daily n=335 %
Adverse Reaction | Any | Grade 3/4 | Any | Grade 3/4
Anemia | 67 | 5 | 58 | 2
Neutropenia | 41 | 32 | 48 | 22
Thrombocytopenia | 3 | 1 | 8 | 1
Febrile Neutropenia | 3 | N/A | 2 | N/A
Infection | 32 | 6 | 20 | 4
Epistaxis | 6 | 0 | 2 | 0
Allergic Reactions | 8 | 1 | 1 | 0
Fluid Retention [Related to treatment] | 24 | 1 | 5 | 0
Weight Gain | 8 | 0 | 3 | 0
Peripheral Edema | 18 | 0 | 2 | 0
Neuropathy Sensory | 30 | 2 | 7 | 0
Neuropathy Motor | 7 | 2 | 3 | 1
Rash/Desquamation | 6 | 0 | 3 | 1
Alopecia | 65 | N/A | 13 | N/A
Nail Changes | 30 | 0 | 8 | 0
Nausea | 41 | 3 | 36 | 2
Diarrhea | 32 | 2 | 10 | 1
Stomatitis/Pharyngitis | 20 | 1 | 8 | 0
Taste Disturbance | 18 | 0 | 7 | 0
Vomiting | 17 | 2 | 14 | 2
Anorexia | 17 | 1 | 14 | 0
Cough | 12 | 0 | 8 | 0
Dyspnea | 15 | 3 | 9 | 1
Cardiac left ventricular function | 10 | 0 | 22 | 1
Fatigue | 53 | 5 | 35 | 5
Myalgia | 15 | 0 | 13 | 1
Tearing | 10 | 1 | 2 | 0
Arthralgia | 8 | 1 | 5 | 1

Gastric Cancer

Combination Therapy with Docetaxel Injection in Gastric Adenocarcinoma

Data in the following table are based on the experience of 221 patients with advanced gastric adenocarcinoma and no history of prior chemotherapy for advanced disease who were treated with Docetaxel Injection 75 mg/m^2 in combination with cisplatin and fluorouracil (see Table 10).

Table 10: Clinically Important Treatment-Emergent Adverse Reactions Regardless of Relationship to Treatment in the Gastric Cancer Study
 | Docetaxel Injection 75 mg/m^2 + cisplatin 75 mg/m^2 + fluorouracil 750 mg/m^2 n=221 |  | Cisplatin 100 mg/m^2 + fluorouracil 1000 mg/m^2 n=224
Adverse Reaction | Any % | Grade 3/4 % | Any % | Grade 3/4 %
Anemia | 97 | 18 | 93 | 26
Neutropenia | 96 | 82 | 83 | 57
Fever in the absence of infection | 36 | 2 | 23 | 1
Thrombocytopenia | 26 | 8 | 39 | 14
Infection | 29 | 16 | 23 | 10
Febrile neutropenia | 16 | N/A | 5 | N/A
Neutropenic infection | 16 | N/A | 10 | N/A
Allergic reactions | 10 | 2 | 6 | 0
Fluid retention [Related to treatment] | 15 | 0 | 4 | 0
Edema | 13 | 0 | 3 | 0
Lethargy | 63 | 21 | 58 | 18
Neurosensory | 38 | 8 | 25 | 3
Neuromotor | 9 | 3 | 8 | 3
Dizziness | 16 | 5 | 8 | 2
Alopecia | 67 | 5 | 41 | 1
Rash/itch | 12 | 1 | 9 | 0
Nail changes | 8 | 0 | 0 | 0
Skin desquamation | 2 | 0 | 0 | 0
Nausea | 73 | 16 | 76 | 19
Vomiting | 67 | 15 | 73 | 19
Anorexia | 51 | 13 | 54 | 12
Stomatitis | 59 | 21 | 61 | 27
Diarrhea | 78 | 20 | 50 | 8
Constipation | 25 | 2 | 34 | 3
Esophagitis/dysphagia/odynophagia | 16 | 2 | 14 | 5
Gastrointestinal pain/cramping | 11 | 2 | 7 | 3
Cardiac dysrhythmias | 5 | 2 | 2 | 1
Myocardial ischemia | 1 | 0 | 3 | 2
Tearing | 8 | 0 | 2 | 0
Altered hearing | 6 | 0 | 13 | 2
Clinically important treatment-emergent adverse reactions were determined based upon frequency, severity, and clinical impact of the adverse reaction.

Head and Neck Cancer

Combination Therapy with Docetaxel Injection in Head and Neck Cancer

Table 11 summarizes the safety data obtained from patients that received induction chemotherapy with Docetaxel Injection 75 mg/m^2 in combination with cisplatin and fluorouracil followed by radiotherapy (TAX323; 174 patients) or chemoradiotherapy (TAX324; 251 patients). The treatment regimens are described in Section 14.6.

Table 11: Clinically Important Treatment-Emergent Adverse Reactions (Regardless of Relationship) in Patients with SCCHN Receiving Induction Chemotherapy with Docetaxel Injection in Combination with Cisplatin and Fluorouracil Followed by Radiotherapy (TAX323) or Chemoradiotherapy (TAX324)
 | TAX323 (n=355) |  |  |  | TAX324 (n=494)
 | Docetaxel Injection arm (n=174) |  | Comparator arm (n=181) |  | Docetaxel Injection arm (n=251) |  | Comparator arm (n=243)
Adverse Reaction (by Body System) | Any % | Grade 3/4 % | Any % | Grade 3/4 % | Any % | Grade 3/4 % | Any % | Grade 3/4 %
Neutropenia | 93 | 76 | 87 | 53 | 95 | 84 | 84 | 56
Anemia | 89 | 9 | 88 | 14 | 90 | 12 | 86 | 10
Thrombocytopenia | 24 | 5 | 47 | 18 | 28 | 4 | 31 | 11
Infection | 27 | 9 | 26 | 8 | 23 | 6 | 28 | 5
Febrile neutropenia [Febrile neutropenia: grade ≥2 fever concomitant with grade 4 neutropenia requiring intravenous antibiotics and/or hospitalization] | 5 | N/A | 2 | N/A | 12 | N/A | 7 | N/A
Neutropenic infection | 14 | N/A | 8 | N/A | 12 | N/A | 8 | N/A
Cancer pain | 21 | 5 | 16 | 3 | 17 | 9 | 20 | 11
Lethargy | 41 | 3 | 38 | 3 | 61 | 5 | 56 | 10
Fever in the absence of infection | 32 | 1 | 37 | 0 | 30 | 4 | 28 | 3
Myalgia | 10 | 1 | 7 | 0 | 7 | 0 | 7 | 2
Weight loss | 21 | 1 | 27 | 1 | 14 | 2 | 14 | 2
Allergy | 6 | 0 | 3 | 0 | 2 | 0 | 0 | 0
Fluid retention [Related to treatment] | 20 | 0 | 14 | 1 | 13 | 1 | 7 | 2
Edema only | 13 | 0 | 7 | 0 | 12 | 1 | 6 | 1
Weight gain only | 6 | 0 | 6 | 0 | 0 | 0 | 1 | 0
Dizziness | 2 | 0 | 5 | 1 | 16 | 4 | 15 | 2
Neurosensory | 18 | 1 | 11 | 1 | 14 | 1 | 14 | 0
Altered hearing | 6 | 0 | 10 | 3 | 13 | 1 | 19 | 3
Neuromotor | 2 | 1 | 4 | 1 | 9 | 0 | 10 | 2
Alopecia | 81 | 11 | 43 | 0 | 68 | 4 | 44 | 1
Rash/itch | 12 | 0 | 6 | 0 | 20 | 0 | 16 | 1
Dry skin | 6 | 0 | 2 | 0 | 5 | 0 | 3 | 0
Desquamation | 4 | 1 | 6 | 0 | 2 | 0 | 5 | 0
Nausea | 47 | 1 | 51 | 7 | 77 | 14 | 80 | 14
Stomatitis | 43 | 4 | 47 | 11 | 66 | 21 | 68 | 27
Vomiting | 26 | 1 | 39 | 5 | 56 | 8 | 63 | 10
Diarrhea | 33 | 3 | 24 | 4 | 48 | 7 | 40 | 3
Constipation | 17 | 1 | 16 | 1 | 27 | 1 | 38 | 1
Anorexia | 16 | 1 | 25 | 3 | 40 | 12 | 34 | 12
Esophagitis/dysphagia/ Odynophagia | 13 | 1 | 18 | 3 | 25 | 13 | 26 | 10
Taste, sense of smell altered | 10 | 0 | 5 | 0 | 20 | 0 | 17 | 1
Gastrointestinal pain/cramping | 8 | 1 | 9 | 1 | 15 | 5 | 10 | 2
Heartburn | 6 | 0 | 6 | 0 | 13 | 2 | 13 | 1
Gastrointestinal bleeding | 4 | 2 | 0 | 0 | 5 | 1 | 2 | 1
Cardiac dysrhythmia | 2 | 2 | 2 | 1 | 6 | 3 | 5 | 3
Venous [Includes superficial and deep vein thrombosis and pulmonary embolism] | 3 | 2 | 6 | 2 | 4 | 2 | 5 | 4
Ischemia myocardial | 2 | 2 | 1 | 0 | 2 | 1 | 1 | 1
Tearing | 2 | 0 | 1 | 0 | 2 | 0 | 2 | 0
Conjunctivitis | 1 | 0 | 1 | 0 | 1 | 0 | 0.4 | 0
Clinically important treatment-emergent adverse reactions based upon frequency, severity, and clinical impact.

6.2 Postmarketing Experience

The following adverse reactions have been identified from clinical trials and/or postmarketing surveillance. Because these reactions are reported from a population of uncertain size, it is not always possible to reliably estimate their frequency or establish a causal relationship to drug exposure.

Body as a whole: diffuse pain, chest pain, radiation recall phenomenon, injection site recall reaction (recurrence of skin reaction at a site of previous extravasation following administration of docetaxel at a different site) at the site of previous extravasation.

Cardiovascular: atrial fibrillation, deep vein thrombosis, ECG abnormalities, thrombophlebitis, pulmonary embolism, syncope, tachycardia, myocardial infarction. Ventricular arrhythmia, including ventricular tachycardia, in patients treated with docetaxel in combination regimens including doxorubicin, 5-fluorouracil and/or cyclophosphamide may be associated with fatal outcome.

Cutaneous: cutaneous lupus erythematosus, bullous eruptions such as erythema multiforme and severe cutaneous adverse reactions (SCARs) such as Stevens-Johnson syndrome, toxic epidermal necrolysis and acute generalized exanthematous pustulosis, scleroderma-like changes (usually preceded by peripheral lymphedema), severe palmar-plantar erythrodysesthesia, and permanent alopecia.

Gastrointestinal: enterocolitis, including colitis, ischemic colitis, and neutropenic enterocolitis, which may be fatal. Abdominal pain, anorexia, constipation, duodenal ulcer, esophagitis, gastrointestinal hemorrhage, gastrointestinal perforation, intestinal obstruction, ileus, and dehydration as a consequence of gastrointestinal events.

Hearing: ototoxicity, hearing disorders and/or hearing loss, including during use with other ototoxic drugs.

Hematologic: bleeding episodes, disseminated intravascular coagulation (DIC), often in association with sepsis or multiorgan failure.

Hepatic: hepatitis, sometimes fatal, primarily in patients with pre-existing liver disorders.

Hypersensitivity: anaphylactic shock with fatal outcome in patients who received premedication. Severe hypersensitivity reactions with fatal outcome with docetaxel in patients who previously experienced hypersensitivity reactions to paclitaxel.

Metabolism and nutrition disorders: electrolyte imbalance, including hyponatremia, hypokalemia, hypomagnesemia, and hypocalcemia. Tumor lysis syndrome, sometimes fatal.

Neurologic: confusion, seizures or transient loss of consciousness, sometimes appearing during the infusion of the drug.

Ophthalmologic: conjunctivitis, lacrimation or lacrimation with or without conjunctivitis, cystoid macular edema (CME). Excessive tearing which may be attributable to lacrimal duct obstruction. Transient visual disturbances (flashes, flashing lights, scotomata), typically occurring during drug infusion and reversible upon discontinuation of the infusion, in association with hypersensitivity reactions.

Respiratory: dyspnea, acute pulmonary edema, acute respiratory distress syndrome/pneumonitis, interstitial lung disease, interstitial pneumonia, respiratory failure, and pulmonary fibrosis, which may be fatal. Radiation pneumonitis in patients receiving concomitant radiotherapy.

Renal: renal insufficiency and renal failure, the majority of cases were associated with concomitant nephrotoxic drugs.

Second primary malignancies: second primary malignancies, including AML, MDS, NHL, and renal cancer [see Warnings and Precautions (5.7)].

Musculoskeletal disorder: myositis.

7 DRUG INTERACTIONS

Docetaxel is a CYP3A4 substrate. In vitro studies have shown that the metabolism of docetaxel may be modified by the concomitant administration of compounds that induce, inhibit, or are metabolized by cytochrome P450 3A4.

In vivo studies showed that the exposure of docetaxel increased 2.2-fold when it was coadministered with ketoconazole, a potent inhibitor of CYP3A4. Protease inhibitors, particularly ritonavir, may increase the exposure of docetaxel. Concomitant use of Docetaxel Injection and drugs that inhibit CYP3A4 may increase exposure to docetaxel and should be avoided. In patients receiving treatment with Docetaxel Injection close monitoring for toxicity and a Docetaxel Injection dose reduction could be considered if systemic administration of a potent CYP3A4 inhibitor cannot be avoided [see Dosage and Administration (2.7), Clinical Pharmacology (12.3)].

8 USE IN SPECIFIC POPULATIONS

8.1 Pregnancy

Risk Summary

Based on findings in animal reproduction studies and its mechanism of action, Docetaxel Injection can cause fetal harm when administered to a pregnant woman [see Clinical Pharmacology (12.1)]. Available data from case reports in the literature and pharmacovigilance with docetaxel use in pregnant women are not sufficient to inform the drug-associated risk of major birth defects, miscarriage, or adverse maternal or fetal outcomes. Docetaxel Injection contains alcohol which can interfere with neurobehavioral development (see Clinical Considerations). In animal reproductive studies, administration of docetaxel to pregnant rats and rabbits during the period of organogenesis caused an increased incidence of embryo-fetal toxicities, including intrauterine mortality, at doses as low as 0.02 and 0.003 times the recommended human dose based on body surface area, respectively (see Data). Advise pregnant women and females of reproductive potential of the potential risk to a fetus.

The estimated background risk of major birth defects and miscarriage for the indicated populations is unknown. All pregnancies have a background risk of birth defect, miscarriage, or other adverse outcomes. In the U.S. general population, the estimated background risk of major birth defects and miscarriage in clinically recognized pregnancies is 2% to 4% and 15% to 20%, respectively.

Clinical Considerations

Docetaxel Injection contains alcohol [see Warnings and Precautions (5.13)]. Published studies have demonstrated that alcohol is associated with fetal harm including central nervous system abnormalities, behavioral disorders, and impaired intellectual development.

Data

Animal data

Intravenous administration of ≥0.3 and 0.03 mg/kg/day docetaxel to pregnant rats and rabbits, respectively, during the period of organogenesis caused an increased incidence of intrauterine mortality, resorptions, reduced fetal weights, and fetal ossification delays. Maternal toxicity was also observed at these doses, which were approximately 0.02 and 0.003 times the daily maximum recommended human dose based on body surface area, respectively.

8.2 Lactation

Risk Summary

There is no information regarding the presence of docetaxel in human milk, or on its effects on milk production or the breastfed child. No lactation studies in animals have been conducted. Because of the potential for serious adverse reactions in a breastfed child, advise women not to breastfeed during treatment with Docetaxel Injection and for 1 week after the last dose.

8.3 Females and Males of Reproductive Potential

Based on findings in animals, Docetaxel Injection can cause fetal harm when administered to a pregnant woman [see Use in Specific Populations (8.1)].

Pregnancy Testing

Verify pregnancy status in females of reproductive potential prior to initiating Docetaxel Injection.

Contraception

Females

Based on genetic toxicity findings, advise females of reproductive potential to use effective contraception during treatment and for 2 months after the last dose of Docetaxel Injection.

Males

Based on genetic toxicity findings, advise male patients with female partners of reproductive potential to use effective contraception during treatment and for 4 months after the last dose of Docetaxel Injection.

Infertility

Based on findings in animal studies, Docetaxel Injection may impair fertility in males of reproductive potential [see Nonclinical Toxicology (13.1)].

8.4 Pediatric Use

The alcohol content of Docetaxel Injection should be taken into account when given to pediatric patients [see Warnings and Precautions (5.13)].

The efficacy of docetaxel in pediatric patients as monotherapy or in combination has not been established. The overall safety profile of docetaxel in pediatric patients receiving monotherapy or TCF was consistent with the known safety profile in adults.

Docetaxel has been studied in a total of 289 pediatric patients: 239 in 2 trials with monotherapy and 50 in combination treatment with cisplatin and 5-fluorouracil (TCF).

Docetaxel Monotherapy

Docetaxel monotherapy was evaluated in a dose-finding phase 1 trial in 61 pediatric patients (median age 12.5 years, range 1–22 years) with a variety of refractory solid tumors. The recommended dose was 125 mg/m^2 as a 1-hour intravenous infusion every 21 days. The primary dose limiting toxicity was neutropenia.

The recommended dose for docetaxel monotherapy was evaluated in a phase 2 single-arm trial in 178 pediatric patients (median age 12 years, range 1–26 years) with a variety of recurrent/refractory solid tumors. Efficacy was not established with tumor response rates ranging from one complete response (CR) (0.6%) in a patient with undifferentiated sarcoma to four partial responses (2.2%) seen in one patient each with Ewing Sarcoma, neuroblastoma, osteosarcoma, and squamous cell carcinoma.

Docetaxel in Combination

Docetaxel was studied in combination with cisplatin and 5-fluorouracil (TCF) versus cisplatin and 5-fluorouracil (CF) for the induction treatment of nasopharyngeal carcinoma (NPC) in pediatric patients prior to chemoradiation consolidation. Seventy-five patients (median age 16 years, range 9 to 21 years) were randomized (2:1) to docetaxel (75 mg/m^2) in combination with cisplatin (75 mg/m^2) and 5-fluorouracil (750 mg/m^2) (TCF) or to cisplatin (80 mg/m^2) and 5-fluorouracil (1000 mg/m^2/day) (CF). The primary endpoint was the CR rate following induction treatment of NPC. One patient out of 50 in the TCF group (2%) had a complete response while none of the 25 patients in the CF group had a complete response.

Pharmacokinetics

Pharmacokinetic parameters for docetaxel were determined in 2 pediatric solid tumor trials. Following docetaxel administration at 55 mg/m^2 to 235 mg/m^2 in a 1-hour intravenous infusion every 3 weeks in 25 patients aged 1 to 20 years (median 11 years), docetaxel clearance was 17.3±10.9 L/h/m^2.

Docetaxel was administered in combination with cisplatin and 5-fluorouracil (TCF), at dose levels of 75 mg/m^2 in a 1-hour intravenous infusion day 1 in 28 patients aged 10 to 21 years (median 16 years, 17 patients were older than 16). Docetaxel clearance was 17.9±8.75 L/h/m^2, corresponding to an AUC of 4.20±2.57 µg∙h/mL.

In summary, the body surface area adjusted clearance of docetaxel monotherapy and TCF combination in children were comparable to those in adults [see Clinical Pharmacology (12.3)].

8.5 Geriatric Use

In general, dose selection for an elderly patient should be cautious, reflecting the greater frequency of decreased hepatic, renal, or cardiac function and of concomitant disease or other drug therapy in elderly patients.

Non-small Cell Lung Cancer

In a study conducted in chemotherapy-naïve patients with NSCLC (TAX326), 148 patients (36%) in the docetaxel+cisplatin group were 65 years of age or greater. There were 128 patients (32%) in the vinorelbine+cisplatin group 65 years of age or greater. In the docetaxel+cisplatin group, patients less than 65 years of age had a median survival of 10.3 months (95% CI: 9.1 months, 11.8 months) and patients 65 years or older had a median survival of 12.1 months (95% CI: 9.3 months, 14 months). In patients 65 years of age or greater treated with docetaxel+cisplatin, diarrhea (55%), peripheral edema (39%) and stomatitis (28%) were observed more frequently than in the vinorelbine+cisplatin group (diarrhea 24%, peripheral edema 20%, stomatitis 20%). Patients treated with docetaxel+cisplatin who were 65 years of age or greater were more likely to experience diarrhea (55%), infections (42%), peripheral edema (39%) and stomatitis (28%) compared to patients less than the age of 65 administered the same treatment (43%, 31%, 31% and 21%, respectively).

When docetaxel was combined with carboplatin for the treatment of chemotherapy-naïve, advanced non-small cell lung carcinoma, patients 65 years of age or greater (28%) experienced higher frequency of infection compared to similar patients treated with docetaxel+cisplatin, and a higher frequency of diarrhea, infection and peripheral edema than elderly patients treated with vinorelbine+cisplatin.

Prostate Cancer

Of the 333 patients treated with docetaxel every three weeks plus prednisone in the prostate cancer study (TAX327), 209 patients were 65 years of age or greater and 68 patients were older than 75 years. In patients treated with docetaxel every three weeks, the following treatment-emergent adverse reactions occurred at rates ≥10% higher in patients 65 years of age or greater compared to younger patients: anemia (71% vs. 59%), infection (37% vs. 24%), nail changes (34% vs. 23%), anorexia (21% vs. 10%), weight loss (15% vs. 5%), respectively.

Breast Cancer

In the adjuvant breast cancer trial (TAX316), docetaxel in combination with doxorubicin and cyclophosphamide was administered to 744 patients of whom 48 (6%) were 65 years of age or greater. The number of elderly patients who received this regimen was not sufficient to determine whether there were differences in safety and efficacy between elderly and younger patients.

Gastric Cancer

Among the 221 patients treated with Docetaxel Injection in combination with cisplatin and fluorouracil in the gastric cancer study, 54 were 65 years of age or older and 2 patients were older than 75 years. In this study, the number of patients who were 65 years of age or older was insufficient to determine whether they respond differently from younger patients. However, the incidence of serious adverse reactions was higher in the elderly patients compared to younger patients. The incidence of the following adverse reactions (all grades, regardless of relationship): lethargy, stomatitis, diarrhea, dizziness, edema, febrile neutropenia/neutropenic infection occurred at rates ≥10% higher in patients who were 65 years of age or older compared to younger patients. Elderly patients treated with TCF should be closely monitored.

Head and Neck Cancer

Among the 174 and 251 patients who received the induction treatment with Docetaxel Injection in combination with cisplatin and fluorouracil (TPF) for SCCHN in the TAX323 and TAX324 studies, 18 (10%) and 32 (13%) of the patients were 65 years of age or older, respectively.

These clinical studies of Docetaxel Injection in combination with cisplatin and fluorouracil in patients with SCCHN did not include sufficient numbers of patients aged 65 and over to determine whether they respond differently from younger patients. Other reported clinical experience with this treatment regimen has not identified differences in responses between elderly and younger patients.

8.6 Hepatic Impairment

Avoid Docetaxel Injection in patients with bilirubin > ULN and patients with AST and/or ALT >1.5 × ULN concomitant with alkaline phosphatase >2.5 × ULN [see Boxed Warning, Warnings and Precautions (5.2), Clinical Pharmacology (12.3)].

The alcohol content of Docetaxel Injection should be taken into account when given to patients with hepatic impairment [see Warnings and Precautions (5.13)].

10 OVERDOSAGE

There is no known antidote for Docetaxel Injection overdosage. In case of overdosage, the patient should be kept in a specialized unit where vital functions can be closely monitored. Anticipated complications of overdosage include: bone marrow suppression, peripheral neurotoxicity, and mucositis. Patients should receive therapeutic G-CSF as soon as possible after discovery of overdose. Other appropriate symptomatic measures should be taken, as needed.

In two reports of overdose, one patient received 150 mg/m^2 and the other received 200 mg/m^2 as 1-hour infusions. Both patients experienced severe neutropenia, mild asthenia, cutaneous reactions, and mild paresthesia, and recovered without incident. In mice, lethality was observed following single intravenous doses that were ≥154 mg/kg (about 4.5 times the human dose of 100 mg/m^2 on a mg/m^2 basis); neurotoxicity associated with paralysis, non-extension of hind limbs, and myelin degeneration was observed in mice at 48 mg/kg (about 1.5 times the human dose of 100 mg/m^2 basis). In male and female rats, lethality was observed at a dose of 20 mg/kg (comparable to the human dose of 100 mg/m^2 on a mg/m^2 basis) and was associated with abnormal mitosis and necrosis of multiple organs.

11 DESCRIPTION

Docetaxel is an antineoplastic agent belonging to the taxoid family. It is prepared by semisynthesis beginning with a precursor extracted from the renewable needle biomass of yew plants. The chemical name for docetaxel is (2R,3S)-N-carboxy-3-phenylisoserine,N-tert-butyl ester, 13-ester with 5β-20-epoxy-1,2α,4,7β,10β,13α-hexahydroxytax-11-en-9-one 4-acetate 2-benzoate, trihydrate. Docetaxel (trihydrate) has the following structural formula:

Docetaxel (trihydrate) is a white to almost-white powder with an empirical formula of C43H53NO14 ∙ 3H2O, and a molecular weight of 861.9. It is highly lipophilic and practically insoluble in water.

Docetaxel Injection, USP is a sterile, non-pyrogenic, pale-yellow to brownish yellow solution at 20 mg/mL concentration.

Each mL contains 20 mg docetaxel (anhydrous), 520 mg polysorbate 80 NF, 7 mg citric acid monohydrate USP, and 395 mg dehydrated alcohol USP.

Docetaxel Injection is available in single-dose vials containing 20 mg (1 mL) or multiple-dose vials containing 80 mg (4 mL) or 160 mg (8 mL) docetaxel (anhydrous).

Docetaxel Injection requires NO prior dilution with a diluent and is ready to add to the infusion solution.

12 CLINICAL PHARMACOLOGY

12.1 Mechanism of Action

Docetaxel is an antineoplastic agent that acts by disrupting the microtubular network in cells that is essential for mitotic and interphase cellular functions. Docetaxel binds to free tubulin and promotes the assembly of tubulin into stable microtubules while simultaneously inhibiting their disassembly. This leads to the production of microtubule bundles without normal function and to the stabilization of microtubules, which results in the inhibition of mitosis in cells. Docetaxel's binding to microtubules does not alter the number of protofilaments in the bound microtubules, a feature which differs from most spindle poisons currently in clinical use.

12.3 Pharmacokinetics

Absorption

The pharmacokinetics of docetaxel has been evaluated in cancer patients after administration of 20 mg/m^2 to 115 mg/m^2 in phase 1 studies. The area under the curve (AUC) was dose proportional following doses of 70 mg/m^2 to 115 mg/m^2 with infusion times of 1 to 2 hours.

Docetaxel’s pharmacokinetic profile is consistent with a three-compartment pharmacokinetic model, with initial rapid distribution phase and the late (terminal) phase.

Distribution

Mean steady state volume of distribution was 113 L. Docetaxel is approximately 94% protein bound in vitro, mainly to α1-acid glycoprotein, albumin, and lipoproteins. In three cancer patients, the in vitro binding to plasma proteins was approximately 97%. Dexamethasone does not affect the protein binding of docetaxel.

Elimination

With extended plasma sampling up to 8 to 22 days post infusion, the estimated mean total body clearance was 18 L/h/m^2 (range of means: 14 to 23) and mean terminal elimination half-life was 116 hours (range of means: 92 to 135).

Metabolism

Docetaxel is metabolized by the CYP3A4 isoenzyme in vitro [see Drug Interactions (7)].

Excretion

In three cancer patients urinary and fecal excretion accounted for approximately 6% and 75% of the administered radioactivity, respectively, within 7 days. About 80% of the radioactivity recovered in feces was excreted during the first 48 hours as 1 major and 3 minor metabolites with less than 8% as unchanged drug.

Specific Populations

Effect of Age

A population pharmacokinetic analysis was carried out after docetaxel treatment of 535 patients dosed at 100 mg/m^2. Pharmacokinetic parameters estimated by this analysis were very close to those estimated from phase 1 studies. The pharmacokinetics of docetaxel was not influenced by age.

Effect of Gender

The population pharmacokinetics analysis described above also indicated that gender did not influence the pharmacokinetics of docetaxel.

Hepatic Impairment

The population pharmacokinetic analysis described above indicated that in patients with clinical chemistry data suggestive of mild to moderate liver impairment (AST and/or ALT >1.5 times ULN concomitant with alkaline phosphatase >2.5 times ULN), total body clearance was lowered by an average of 27%, resulting in a 38% increase in systemic exposure (AUC). This average, however, includes a substantial range and there is, at present, no measurement that would allow recommendation for dose adjustment in such patients. Patients with combined abnormalities of transaminase and alkaline phosphatase should not be treated with Docetaxel Injection. Patients with severe hepatic impairment have not been studied [see Warnings and Precautions (5.2), Use in Specific Populations (8.6)].

Effect of Race

Mean total body clearance for Japanese patients dosed at the range of 10 mg/m^2 to 90 mg/m^2 was similar to that of European/American populations dosed at 100 mg/m^2, suggesting no significant difference in the elimination of docetaxel in the two populations.

Drug Interaction Studies

Effect of Ketoconazole

The effect of ketoconazole (a strong CYP3A4 inhibitor) on the pharmacokinetics of docetaxel was investigated in 7 cancer patients. Patients were randomized to receive either docetaxel (100 mg/m^2 intravenous) alone or docetaxel (10 mg/m^2 intravenous) in combination with ketoconazole (200 mg orally once daily for 3 days) in a crossover design with a 3-week washout period. The results of this study indicated that the mean dose-normalized AUC of docetaxel was increased 2.2-fold and its clearance was reduced by 49% when docetaxel was coadministered with ketoconazole [see Dosage and Administration (2.7), Drug Interactions (7)].

Effect of Combination Therapies

- Dexamethasone: Docetaxel total body clearance was not modified by pretreatment with dexamethasone.
- Cisplatin: Clearance of docetaxel in combination therapy with cisplatin was similar to that previously observed following monotherapy with docetaxel. The pharmacokinetic profile of cisplatin in combination therapy with docetaxel was similar to that observed with cisplatin alone.
- Cisplatin and Fluorouracil: The combined administration of docetaxel, cisplatin and fluorouracil in 12 patients with solid tumors had no influence on the pharmacokinetics of each individual drug.
- Prednisone: A population pharmacokinetic analysis of plasma data from 40 patients with metastatic castration-resistant prostate cancer indicated that docetaxel systemic clearance in combination with prednisone is similar to that observed following administration of docetaxel alone.
- Cyclophosphamide and Doxorubicin: A study was conducted in 30 patients with advanced breast cancer to determine the potential for drug-drug interactions between docetaxel (75 mg/m^2), doxorubicin (50 mg/m^2), and cyclophosphamide (500 mg/m^2) when administered in combination. The coadministration of docetaxel had no effect on the pharmacokinetics of doxorubicin and cyclophosphamide when the three drugs were given in combination compared to coadministration of doxorubicin and cyclophosphamide only. In addition, doxorubicin and cyclophosphamide had no effect on docetaxel plasma clearance when the three drugs were given in combination compared to historical data for docetaxel monotherapy.

13 NONCLINICAL TOXICOLOGY

13.1 Carcinogenesis, Mutagenesis, Impairment of Fertility

Carcinogenicity studies with docetaxel have not been performed.

Docetaxel was genotoxic by an aneugenic mechanism in the in vitro chromosome aberration test in CHO-K1 cells and in the in vivo micronucleus test in mice administered doses of 0.39 to 1.56 mg/kg (about 1/60th to 1/15th the recommended human dose on a mg/m^2 basis). Docetaxel was not mutagenic in the Ames test or the CHO/HGPRT gene mutation assays.

Docetaxel did not reduce fertility in rats when administered in multiple intravenous doses of up to 0.3 mg/kg (about 1/50th the recommended human dose on a mg/m^2 basis), but decreased testicular weights were reported. This correlates with findings of a 10-cycle toxicity study (dosing once every 21 days for 6 months) in rats and dogs in which testicular atrophy or degeneration was observed at intravenous doses of 5 mg/kg in rats and 0.375 mg/kg in dogs (about 1/3rd and 1/15th the recommended human dose on a mg/m^2 basis, respectively). An increased frequency of dosing in rats produced similar effects at lower dose levels.

14 CLINICAL STUDIES

14.1 Locally Advanced or Metastatic Breast Cancer

The efficacy and safety of docetaxel have been evaluated in locally advanced or metastatic breast cancer after failure of previous chemotherapy (alkylating agent-containing regimens or anthracycline-containing regimens).

Randomized Trials

In one randomized trial, patients with a history of prior treatment with an anthracycline-containing regimen were assigned to treatment with docetaxel (100 mg/m^2 every 3 weeks) or the combination of mitomycin (12 mg/m^2 every 6 weeks) and vinblastine (6 mg/m^2 every 3 weeks). Two hundred three patients were randomized to docetaxel and 189 to the comparator arm. Most patients had received prior chemotherapy for metastatic disease; only 27 patients on the docetaxel arm and 33 patients on the comparator arm entered the study following relapse after adjuvant therapy. Three-quarters of patients had measurable, visceral metastases. The primary endpoint was time to progression. The following table summarizes the study results (see Table 12).

Table 12: Efficacy of Docetaxel in the Treatment of Breast Cancer Patients Previously Treated with an Anthracycline-Containing Regimen (Intent-to-Treat Analysis)
Efficacy Parameter | Docetaxel (n=203) | Mitomycin/Vinblastine (n=189) | p-value
Median Survival | 11.4 months | 8.7 months | p=0.01 Log Rank
Risk Ratio [For the risk ratio, a value less than 1.00 favors docetaxel.] , Mortality (Docetaxel: Control) 95% CI (Risk Ratio) | 0.73 0.58–0.93 |  | p=0.01 Log Rank
Median Time to Progression | 4.3 months | 2.5 months | p=0.01 Log Rank
Risk Ratio,; Progression; (Docetaxel: Control) 95% CI (Risk Ratio) | 0.75 0.61–0.94 |  | p=0.01 Log Rank
Overall Response Rate; Complete Response Rate | 28.1%; 3.4% | 9.5%; 1.6% | p<0.0001; Chi Square

In a second randomized trial, patients previously treated with an alkylating-containing regimen were assigned to treatment with docetaxel (100 mg/m^2) or doxorubicin (75 mg/m^2) every 3 weeks. One hundred sixty-one patients were randomized to docetaxel and 165 patients to doxorubicin. Approximately one-half of patients had received prior chemotherapy for metastatic disease, and one-half entered the study following relapse after adjuvant therapy. Three-quarters of patients had measurable, visceral metastases. The primary endpoint was time to progression. The study results are summarized below (see Table 13).

Table 13: Efficacy of Docetaxel in the Treatment of Breast Cancer Patients Previously Treated with an Alkylating-Containing Regimen (Intent-to-Treat Analysis)
Efficacy Parameter | Docetaxel; (n=161) | Doxorubicin; (n=165) | p-value
Median Survival | 14.7 months | 14.3 months | p=0.39 Log Rank
Risk Ratio [For the risk ratio, a value less than 1.00 favors docetaxel.] , Mortality (Docetaxel: Control) 95% CI (Risk Ratio) | 0.89 0.68–1.16 |  | p=0.39 Log Rank
Median Time to Progression | 6.5 months | 5.3 months | p=0.45 Log Rank
Risk Ratio, Progression (Docetaxel: Control) 95% CI (Risk Ratio) | 0.93 0.71–1.16 |  | p=0.45 Log Rank
Overall Response Rate; Complete Response Rate | 45.3%; 6.8% | 29.7%; 4.2% | p=0.004; Chi Square

In another multicenter open-label, randomized trial (TAX313), in the treatment of patients with advanced breast cancer who progressed or relapsed after one prior chemotherapy regimen, 527 patients were randomized to receive docetaxel monotherapy 60 mg/m^2 (n=151), 75 mg/m^2 (n=188) or 100 mg/m^2 (n=188). In this trial, 94% of patients had metastatic disease and 79% had received prior anthracycline therapy. Response rate was the primary endpoint. Response rates increased with docetaxel dose: 19.9% for the 60 mg/m^2 group compared to 22.3% for the 75 mg/m^2 and 29.8% for the 100 mg/m^2 group; pair-wise comparison between the 60 mg/m^2 and 100 mg/m^2 groups was statistically significant (p=0.037).

Single Arm Studies

Docetaxel at a dose of 100 mg/m^2 was studied in six single arm studies involving a total of 309 patients with metastatic breast cancer in whom previous chemotherapy had failed. Among these, 190 patients had anthracycline-resistant breast cancer, defined as progression during an anthracycline-containing chemotherapy regimen for metastatic disease, or relapse during an anthracycline-containing adjuvant regimen. In anthracycline-resistant patients, the overall response rate was 37.9% (72/190; 95% CI: 31.0–44.8) and the complete response rate was 2.1%.

Docetaxel was also studied in three single arm Japanese studies at a dose of 60 mg/m^2, in 174 patients who had received prior chemotherapy for locally advanced or metastatic breast cancer. Among 26 patients whose best response to an anthracycline had been progression, the response rate was 34.6% (95% CI: 17.2–55.7), similar to the response rate in single arm studies of 100 mg/m^2.

14.2 Adjuvant Treatment of Breast Cancer

A multicenter, open-label, randomized trial (TAX316) evaluated the efficacy and safety of docetaxel for the adjuvant treatment of patients with axillary-node-positive breast cancer and no evidence of distant metastatic disease. After stratification according to the number of positive lymph nodes (1–3, 4+), 1491 patients were randomized to receive either docetaxel 75 mg/m^2 administered 1-hour after doxorubicin 50 mg/m^2 and cyclophosphamide 500 mg/m^2 (TAC arm), or doxorubicin 50 mg/m^2 followed by fluorouracil 500 mg/m^2 and cyclophosphamide 500 mg/m^2 (FAC arm). Both regimens were administered every 3 weeks for 6 cycles. Docetaxel was administered as a 1-hour infusion; all other drugs were given as intravenous bolus on day 1. In both arms, after the last cycle of chemotherapy, patients with positive estrogen and/or progesterone receptors received tamoxifen 20 mg daily for up to 5 years. Adjuvant radiation therapy was prescribed according to guidelines in place at participating institutions and was given to 69% of patients who received TAC and 72% of patients who received FAC.

Results from a second interim analysis (median follow-up 55 months) are as follows: In study TAX316, the docetaxel-containing combination regimen TAC showed significantly longer disease-free survival (DFS) than FAC (hazard ratio=0.74; 2-sided 95% CI=0.60, 0.92, stratified log rank p=0.0047). The primary endpoint, disease-free survival, included local and distant recurrences, contralateral breast cancer and deaths from any cause. The overall reduction in risk of relapse was 25.7% for TAC-treated patients (see Figure 1).

At the time of this interim analysis, based on 219 deaths, overall survival was longer for TAC than FAC (hazard ratio=0.69, 2-sided 95% CI=0.53, 0.90) (see Figure 2). There will be further analysis at the time survival data mature.

The following table describes the results of subgroup analyses for DFS and OS (see Table 14).

Table 14: Subset Analyses-Adjuvant Breast Cancer Study
 |  | Disease Free Survival |  | Overall Survival
Patient subset | Number of patients | Hazard ratio [A hazard ratio of less than 1 indicates that TAC is associated with a longer disease free survival or overall survival compared to FAC.] | 95% CI | Hazard ratio | 95% CI
No. of positive nodes
Overall | 744 | 0.74 | (0.60, 0.92) | 0.69 | (0.53, 0.90)
1–3 | 467 | 0.64 | (0.47, 0.87) | 0.45 | (0.29, 0.70)
4+ | 277 | 0.84 | (0.63, 1.12) | 0.93 | (0.66, 1.32)
Receptor status
Positive | 566 | 0.76 | (0.59, 0.98) | 0.69 | (0.48, 0.99)
Negative | 178 | 0.68 | (0.48, 0.97) | 0.66 | (0.44, 0.98)

14.3 Non-small Cell Lung Cancer (NSCLC)

The efficacy and safety of docetaxel has been evaluated in patients with unresectable, locally advanced or metastatic non-small cell lung cancer whose disease has failed prior platinum-based chemotherapy or in patients who are chemotherapy-naïve.

Monotherapy with Docetaxel for NSCLC Previously Treated with Platinum-Based Chemotherapy

Two randomized, controlled trials established that a docetaxel dose of 75 mg/m^2 was tolerable and yielded a favorable outcome in patients previously treated with platinum-based chemotherapy (see below). Docetaxel at a dose of 100 mg/m^2, however, was associated with unacceptable hematologic toxicity, infections, and treatment-related mortality and this dose should not be used [see Boxed Warning, Dosage and Administration (2.7), Warnings and Precautions (5.3)].

One trial (TAX317), randomized patients with locally advanced or metastatic non-small cell lung cancer, a history of prior platinum-based chemotherapy, no history of taxane exposure, and an ECOG performance status ≤2 to docetaxel or best supportive care. The primary endpoint of the study was survival. Patients were initially randomized to docetaxel 100 mg/m^2 or best supportive care, but early toxic deaths at this dose led to a dose reduction to docetaxel 75 mg/m^2. A total of 104 patients were randomized in this amended study to either docetaxel 75 mg/m^2 or best supportive care.

In a second randomized trial (TAX320), 373 patients with locally advanced or metastatic non-small cell lung cancer, a history of prior platinum-based chemotherapy, and an ECOG performance status ≤2 were randomized to docetaxel 75 mg/m^2, docetaxel 100 mg/m^2 and a treatment in which the investigator chose either vinorelbine 30 mg/m^2 days 1, 8, and 15 repeated every 3 weeks or ifosfamide 2 g/m^2 days 1–3 repeated every 3 weeks. Forty percent of the patients in this study had a history of prior paclitaxel exposure. The primary endpoint was survival in both trials. The efficacy data for the docetaxel 75 mg/m^2 arm and the comparator arms are summarized in Table 15 and Figures 3 and 4 showing the survival curves for the two studies.

Table 15: Efficacy of Docetaxel in the Treatment of Non-small Cell Lung Cancer Patients Previously Treated with a Platinum-Based Chemotherapy Regimen (Intent-to-Treat Analysis)
 | TAX317 |  | TAX320
 | Docetaxel 75 mg/m^2 n=55 | Best Supportive Care n=49 | Docetaxel 75 mg/m^2 n=125 | Control (V/I [Vinorelbine/Ifosfamide]) n=123
Overall Survival; Log-rank Test | p=0.01 |  | p=0.13
Risk Ratio [a value less than 1.00 favors docetaxel] , Mortality (Docetaxel: Control) 95% CI (Risk Ratio) | 0.56 (0.35, 0.88) |  | 0.82 (0.63, 1.06)
Median Survival 95% CI | 7.5 months [p≤0.05] (5.5, 12.8) | 4.6 months (3.7, 6.1) | 5.7 months (5.1, 7.1) | 5.6 months (4.4, 7.9)
% 1-year Survival 95% CI | 37% [uncorrected for multiple comparisons] (24, 50) | 12% (2, 23) | 30% (22, 39) | 20% (13, 27)
Time to Progression 95% CI | 12.3 weeks (9.0, 18.3) | 7.0 weeks (6.0, 9.3) | 8.3 weeks (7.0, 11.7) | 7.6 weeks (6.7, 10.1)
Response Rate 95% CI | 5.5% (1.1, 15.1) | Not Applicable | 5.7% (2.3, 11.3) | 0.8% (0.0, 4.5)

Only one of the two trials (TAX317) showed a clear effect on survival, the primary endpoint; that trial also showed an increased rate of survival to one year. In the second study (TAX320) the rate of survival at one year favored docetaxel 75 mg/m^2.

Patients treated with docetaxel at a dose of 75 mg/m^2 experienced no deterioration in performance status and body weight relative to the comparator arms used in these trials.

Combination Therapy with Docetaxel for Chemotherapy-Naïve NSCLC

In a randomized controlled trial (TAX326), 1218 patients with unresectable stage IIIB or IV NSCLC and no prior chemotherapy were randomized to receive one of three treatments: docetaxel 75 mg/m^2 as a 1 hour infusion immediately followed by cisplatin 75 mg/m^2 over 30 to 60 minutes every 3 weeks; vinorelbine 25 mg/m^2 administered over 6 – 10 minutes on days 1, 8, 15, 22 followed by cisplatin 100 mg/m^2 administered on day 1 of cycles repeated every 4 weeks; or a combination of docetaxel and carboplatin.

The primary efficacy endpoint was overall survival. Treatment with docetaxel+cisplatin did not result in a statistically significantly superior survival compared to vinorelbine+cisplatin (see table below). The 95% confidence interval of the hazard ratio (adjusted for interim analysis and multiple comparisons) shows that the addition of docetaxel to cisplatin results in an outcome ranging from a 6% inferior to a 26% superior survival compared to the addition of vinorelbine to cisplatin. The results of a further statistical analysis showed that at least (the lower bound of the 95% confidence interval) 62% of the known survival effect of vinorelbine when added to cisplatin (about a 2-month increase in median survival; Wozniak et al. JCO, 1998) was maintained. The efficacy data for the docetaxel+cisplatin arm and the comparator arm are summarized in Table 16.

Table 16: Survival Analysis of Docetaxel in Combination Therapy for Chemotherapy-Naïve NSCLC
Comparison | Docetaxel + Cisplatin n=408 | Vinorelbine + Cisplatin n=405
Kaplan-Meier Estimate of Median Survival | 10.9 months | 10.0 months
p-value [From the superiority test (stratified log rank) comparing docetaxel+cisplatin to vinorelbine+cisplatin] | 0.122
Estimated Hazard Ratio [Hazard ratio of docetaxel+cisplatin versus vinorelbine+cisplatin. A hazard ratio of less than 1 indicates that docetaxel+cisplatin is associated with a longer survival.] | 0.88
Adjusted 95% CI [Adjusted for interim analysis and multiple comparisons.] | (0.74, 1.06)

The second comparison in the same three-arm study, vinorelbine+cisplatin versus docetaxel+carboplatin, did not demonstrate superior survival associated with the docetaxel arm (Kaplan-Meier estimate of median survival was 9.1 months for docetaxel+carboplatin compared to 10.0 months on the vinorelbine+cisplatin arm) and the docetaxel+carboplatin arm did not demonstrate preservation of at least 50% of the survival effect of vinorelbine added to cisplatin. Secondary endpoints evaluated in the trial included objective response and time to progression. There was no statistically significant difference between docetaxel+cisplatin and vinorelbine+cisplatin with respect to objective response and time to progression (see Table 17).

Table 17: Response and TTP Analysis of Docetaxel in Combination Therapy for Chemotherapy-Naïve NSCLC
Endpoint | Docetaxel + Cisplatin | Vinorelbine + Cisplatin | p-value
Objective Response Rate (95% CI) [Adjusted for multiple comparisons.] | 31.6% (26.5%, 36.8%) | 24.4% (19.8%, 29.2%) | Not Significant
Median Time to Progression [Kaplan-Meier estimates.] (95% CI) | 21.4 weeks (19.3, 24.6) | 22.1 weeks (18.1, 25.6) | Not Significant

14.4 Castration-Resistant Prostate Cancer

The safety and efficacy of docetaxel in combination with prednisone in patients with metastatic castration-resistant prostate cancer were evaluated in a randomized multicenter active control trial. A total of 1006 patients with Karnofsky Performance Status (KPS) ≥60 were randomized to the following treatment groups:

- Docetaxel 75 mg/m^2 every 3 weeks for 10 cycles.
- Docetaxel 30 mg/m^2 administered weekly for the first 5 weeks in a 6-week cycle for 5 cycles.
- Mitoxantrone 12 mg/m^2 every 3 weeks for 10 cycles.

All 3 regimens were administered in combination with prednisone 5 mg twice daily, continuously.

In the docetaxel every three week arm, a statistically significant overall survival advantage was demonstrated compared to mitoxantrone. In the docetaxel weekly arm, no overall survival advantage was demonstrated compared to the mitoxantrone control arm. Efficacy results for the docetaxel every 3 week arm versus the control arm are summarized in Table 18 and Figure 5.

Table 18: Efficacy of Docetaxel in the Treatment of Patients with Metastatic Castration-Resistant Prostate Cancer (Intent-to-Treat Analysis)
 | Docetaxel + Prednisone every 3 weeks | Mitoxantrone + Prednisone every 3 weeks
Number of patients | 335 | 337
Median survival (months) | 18.9 | 16.5
95% CI | (17.0–21.2) | (14.4–18.6)
Hazard ratio | 0.761 | —
95% CI | (0.619–0.936) | —
p-value [Stratified log-rank test. Threshold for statistical significance = 0.0175 because of 3 arms.] | 0.0094 | —

14.5 Gastric Adenocarcinoma

A multicenter, open-label, randomized trial was conducted to evaluate the safety and efficacy of Docetaxel Injection for the treatment of patients with advanced gastric adenocarcinoma, including adenocarcinoma of the gastroesophageal junction, who had not received prior chemotherapy for advanced disease. A total of 445 patients with KPS >70 were treated with either Docetaxel Injection (T) (75 mg/m^2 on day 1) in combination with cisplatin (C) (75 mg/m^2 on day 1) and fluorouracil (F) (750 mg/m^2 per day for 5 days) or cisplatin (100 mg/m^2 on day 1) and fluorouracil (1000 mg/m^2 per day for 5 days). The length of a treatment cycle was 3 weeks for the TCF arm and 4 weeks for the CF arm. The demographic characteristics were balanced between the two treatment arms. The median age was 55 years, 71% were male, 71% were Caucasian, 24% were 65 years of age or older, 19% had a prior curative surgery and 12% had palliative surgery. The median number of cycles administered per patient was 6 (with a range of 1–16) for the TCF arm compared to 4 (with a range of 1–12) for the CF arm. Time to progression (TTP) was the primary endpoint and was defined as time from randomization to disease progression or death from any cause within 12 weeks of the last evaluable tumor assessment or within 12 weeks of the first infusion of study drugs for patients with no evaluable tumor assessment after randomization. The hazard ratio (HR) for TTP was 1.47 (CF/TCF, 95% CI: 1.19–1.83) with a significantly longer TTP (p=0.0004) in the TCF arm. Approximately 75% of patients had died at the time of this analysis. Overall survival was significantly longer (p=0.0201) in the TCF arm with a HR of 1.29 (95% CI: 1.04–1.61). Efficacy results are summarized in Table 19 and Figures 6 and 7.

Table 19: Efficacy of Docetaxel Injection in the Treatment of Patients with Gastric Adenocarcinoma
Endpoint | TCF n=221 | CF n=224
Median TTP (months) (95% CI) | 5.6 (4.86–5.91) | 3.7 (3.45–4.47)
Hazard ratio [For the hazard ratio (TCF/CF), values less than 1.00 favor the Docetaxel Injection arm.] (95% CI) [Unstratified log-rank test] p-value | 0.68 (0.55–0.84) 0.0004
Median survival (months) (95% CI) | 9.2 (8.38–10.58) | 8.6 (7.16–9.46)
Hazard ratio (95% CI) p-value | 0.77 (0.62–0.96) 0.0201
Overall Response Rate (CR+PR) (%) | 36.7 | 25.4
p-value | 0.0106

Subgroup analyses were consistent with the overall results across age, gender and race.

14.6 Head and Neck Cancer

Induction Chemotherapy Followed by Radiotherapy (TAX323)

The safety and efficacy of Docetaxel Injection in the induction treatment of patients with squamous cell carcinoma of the head and neck (SCCHN) was evaluated in a multicenter, open-label, randomized trial (TAX323). In this study, 358 patients with inoperable locally advanced SCCHN, and WHO performance status 0 or 1, were randomized to one of two treatment arms. Patients on the Docetaxel Injection arm received Docetaxel Injection (T) 75 mg/m^2 followed by cisplatin (P) 75 mg/m^2 on Day 1, followed by fluorouracil (F) 750 mg/m^2 per day as a continuous infusion on Days 1–5. The cycles were repeated every three weeks for 4 cycles. Patients whose disease did not progress received radiotherapy (RT) according to institutional guidelines (TPF/RT). Patients on the comparator arm received cisplatin (P) 100 mg/m^2 on Day 1, followed by fluorouracil (F) 1000 mg/m^2/day as a continuous infusion on Days 1–5. The cycles were repeated every three weeks for 4 cycles. Patients whose disease did not progress received RT according to institutional guidelines (PF/RT). At the end of chemotherapy, with a minimal interval of 4 weeks and a maximal interval of 7 weeks, patients whose disease did not progress received radiotherapy (RT) according to institutional guidelines. Locoregional therapy with radiation was delivered either with a conventional fraction regimen (1.8 Gy–2.0 Gy once a day, 5 days per week for a total dose of 66 to 70 Gy) or with an accelerated/hyperfractionated regimen (twice a day, with a minimum interfraction interval of 6 hours, 5 days per week, for a total dose of 70 to 74 Gy, respectively). Surgical resection was allowed following chemotherapy, before or after radiotherapy.

The primary endpoint in this study, progression-free survival (PFS), was significantly longer in the TPF arm compared to the PF arm, p=0.0077 (median PFS: 11.4 vs. 8.3 months, respectively) with an overall median follow-up time of 33.7 months. Median overall survival with a median follow-up of 51.2 months was also significantly longer in favor of the TPF arm compared to the PF arm (median OS: 18.6 vs. 14.2 months, respectively). Efficacy results are presented in Table 20 and Figures 8 and 9.

Table 20: Efficacy of Docetaxel Injection in the Induction Treatment of Patients with Inoperable Locally Advanced SCCHN (Intent-to-Treat Analysis)
Endpoint | Docetaxel Injection + Cisplatin + Fluorouracil n=177 | Cisplatin + Fluorouracil n=181
Median progression free survival (months) (95% CI) | 11.4 (10.1–14.0) | 8.3 (7.4–9.1)
Adjusted Hazard ratio (95% CI) [Stratified log-rank test based on primary tumor site] p-value | 0.71 (0.56–0.91) 0.0077
Median survival (months) (95% CI) | 18.6 (15.7–24.0) | 14.2 (11.5–18.7)
Hazard ratio (95% CI) [Stratified log-rank test, not adjusted for multiple comparisons] p-value | 0.71 (0.56–0.90) 0.0055
Best overall response (CR + PR) to chemotherapy (%) | 67.8 (60.4–74.6) | 53.6 (46.0–61.0)
(95% CI) [Chi square test, not adjusted for multiple comparisons] p-value | 0.006
Best overall response (CR + PR) to study treatment [chemotherapy +/- radiotherapy] (%) | 72.3 (65.1–78.8) | 58.6 (51.0–65.8)
(95% CI) p-value | 0.006
A Hazard ratio of less than 1 favors Docetaxel Injection+cisplatin+fluorouracil

Induction Chemotherapy Followed by Chemoradiotherapy (TAX324)

The safety and efficacy of Docetaxel Injection in the induction treatment of patients with locally advanced (unresectable, low surgical cure, or organ preservation) SCCHN was evaluated in a randomized, multicenter open-label trial (TAX324). In this study, 501 patients, with locally advanced SCCHN, and a WHO performance status of 0 or 1, were randomized to one of two treatment arms. Patients on the Docetaxel Injection arm received Docetaxel Injection (T) 75 mg/m^2 by intravenous infusion on day 1 followed by cisplatin (P) 100 mg/m^2 administered as a 30-minute to three-hour intravenous infusion, followed by the continuous intravenous infusion of fluorouracil (F) 1000 mg/m^2/day from day 1 to day 4. The cycles were repeated every 3 weeks for 3 cycles. Patients on the comparator arm received cisplatin (P) 100 mg/m^2 as a 30-minute to three-hour intravenous infusion on day 1 followed by the continuous intravenous infusion of fluorouracil (F) 1000 mg/m^2/day from day 1 to day 5. The cycles were repeated every 3 weeks for 3 cycles.

All patients in both treatment arms who did not have progressive disease were to receive 7 weeks of chemoradiotherapy (CRT) following induction chemotherapy 3 to 8 weeks after the start of the last cycle. During radiotherapy, carboplatin (AUC 1.5) was given weekly as a one-hour intravenous infusion for a maximum of 7 doses. Radiation was delivered with megavoltage equipment using once daily fractionation (2 Gy per day, 5 days per week for 7 weeks for a total dose of 70–72 Gy). Surgery on the primary site of disease and/or neck could be considered at anytime following completion of CRT.

The primary efficacy endpoint, overall survival (OS), was significantly longer (log-rank test, p = 0.0058) with the Docetaxel Injection-containing regimen compared to PF [median OS: 70.6 vs. 30.1 months, respectively, hazard ratio (HR) = 0.70, 95% confidence interval (CI) = 0.54–0.90]. Overall survival results are presented in Table 21 and Figure 10.

Table 21: Efficacy of Docetaxel Injection in the Induction Treatment of Patients with Locally Advanced SCCHN (Intent-to-Treat Analysis)
Endpoint | Docetaxel Injection + Cisplatin + Fluorouracil n=255 | Cisplatin + Fluorouracil n=246
Median overall survival (months) (95% CI) | 70.6 (49.0–NE) | 30.1 (20.9–51.5)
Hazard ratio: (95% CI) [unadjusted log-rank test] p-value | 0.70 (0.54–0.90) 0.0058
A Hazard ratio of less than 1 favors Docetaxel Injection+cisplatin+fluorouracil
NE - not estimable

15 REFERENCES

1. "OSHA Hazardous Drugs." http://www.osha.gov/SLTC/hazardousdrugs/index.html

16 HOW SUPPLIED/STORAGE AND HANDLING

16.1 How Supplied

Docetaxel Injection, USP is supplied in single-dose or multiple-dose vials as a sterile, pyrogen-free, non-aqueous pale-yellow to brownish yellow solution. Discard unused portion of the single-dose vial.

The following strengths are available in a one-vial formulation:

Unit of Sale | Concentration
NDC 0409-4235-01; Carton of 1 single-dose vial | 20 mg/mL
NDC 0409-5068-01; Carton of 1 multiple-dose vial | 80 mg/4 mL; (20 mg/mL)
NDC 0409-0365-01; Carton of 1 multiple-dose vial | 160 mg/8 mL; (20 mg/mL)

16.2 Storage

Store between 2°C and 25°C (36°F and 77°F). Retain in the original package to protect from light. Freezing does not adversely affect the product.

After first use and following multiple needle entries and product withdrawals, Docetaxel Injection multiple-dose vials are stable for up to 28 days when stored between 2°C and 8°C (36°F and 46°F) and protected from light.

16.3 Handling and Disposal

Docetaxel Injection is a hazardous drug. Follow applicable special handling and disposal procedures.^1

17 PATIENT COUNSELING INFORMATION

Advise the patient to read the FDA-approved patient labeling (Patient Information).

Bone Marrow Suppression

Advise patients that periodic assessment of their blood count will be performed to detect neutropenia, thrombocytopenia, and/or anemia [see Contraindications (4), Warnings and Precautions (5.3)]. Instruct patients to monitor their temperature frequently and immediately report any occurrence of fever.

Enterocolitis and Neutropenic Colitis

Advise patients of the symptoms of colitis, such as abdominal pain or tenderness, and/or diarrhea, with or without fever, and instruct patients to promptly contact their healthcare provider if they experience these symptoms [see Dosage and Administration (2.7), Warnings and Precautions (5.4)].

Hypersensitivity Reactions

Ask patients whether they have previously received paclitaxel therapy, and if they have experienced a hypersensitivity reaction to paclitaxel. Instruct patients to immediately report to their healthcare provider signs of a hypersensitivity reaction [see Contraindications (4), Warnings and Precautions (5.5)].

Fluid Retention

Advise patients to report signs of fluid retention such as peripheral edema in the lower extremities, weight gain, and dyspnea immediately to their healthcare provider [see Warnings and Precautions (5.6)].

Second Primary Malignancies

Advise patients on the risk of second primary malignancies during treatment with Docetaxel Injection [see Warnings and Precautions (5.7)].

Cutaneous Reactions

Advise patients that localized erythema of the extremities and severe skin toxicities may occur. Instruct patients to immediately report severe cutaneous reactions to their healthcare provider [see Dosage and Administration (2.7), Warnings and Precautions (5.8)].

Neurologic Reactions

Advise patients that neurosensory symptoms or peripheral neuropathy may occur. Instruct patients to immediately report neurologic reactions to their healthcare provider [see Dosage and Administration (2.7), Warnings and Precautions (5.9)].

Eye Disorders

Advise patients that vision disturbances and excessive tearing are associated with Docetaxel Injection administration. Instruct patients to immediately report any vision changes to their healthcare provider [see Warnings and Precautions (5.10)].

Gastrointestinal Reactions

Explain to patients that nausea, vomiting, diarrhea, and constipation are associated with Docetaxel Injection administration. Instruct patients to report any severe events to their healthcare provider [see Adverse Reactions (6)].

Cardiac Disorders

Advise patients to report any irregular and/or rapid heartbeat, severe shortness of breath, dizziness, and/or fainting immediately to their healthcare provider [see Adverse Reactions (6)].

Other Common Adverse Reactions

Advise patients that other common adverse reactions associated with Docetaxel Injection may include alopecia (cases of permanent hair loss have been reported), asthenia, anorexia, dysgeusia, mucositis, myalgia, nail disorders, or pain. Instruct patients to report these reactions to their healthcare provider if serious events occur [see Adverse Reactions (6)].

Importance of Corticosteroids

Explain the significance of oral corticosteroids such as dexamethasone administration to the patient to help facilitate compliance. Instruct patients to report to their healthcare provider if they were not compliant with the oral corticosteroid regimen [see Dosage and Administration (2.6)].

Embryo-Fetal Toxicity

Docetaxel Injection can cause fetal harm. Advise patients to inform their healthcare provider of a known or suspected pregnancy. Advise patients to avoid becoming pregnant while receiving this drug. Advise female patients of reproductive potential to use effective contraceptives during treatment and for 2 months after the last dose of Docetaxel Injection. Advise male patients with female partners of reproductive potential to use effective contraception during treatment and for 4 months after the last dose of Docetaxel Injection [see Warnings and Precautions (5.12), Use in Specific Populations (8.1, 8.3)].

Lactation

Advise women not to breastfeed during Docetaxel Injection treatment and for 1 week after the last dose [see Use in Specific Populations (8.2)].

Infertility

Advise males of reproductive potential that Docetaxel Injection may impair fertility [see Nonclinical Toxicology (13.1)].

Alcohol Content in Docetaxel Injection

Explain to patients the possible effects of the alcohol content in Docetaxel Injection, including possible effects on the central nervous system [see Warnings and Precautions (5.13)].

Tumor Lysis Syndrome

Advise patients of the potential risk of tumor lysis syndrome and to immediately report any signs or symptoms associated with this event (nausea, vomiting, confusion, shortness of breath, seizure, irregular heartbeat, dark or cloudy urine, reduced amount of urine, unusual tiredness, muscle cramps) to their healthcare provider. Advise patients of the importance of keeping scheduled appointment for blood work or other laboratory tests and of drinking adequate fluids to avoid dehydration. [see Warnings and Precautions (5.14)].

Ability to Drive or Operate Machines

Explain to patients that Docetaxel Injection may impair their ability to drive or operate machines due to its side effects [see Adverse Reactions (6)] or due to the alcohol content of Docetaxel Injection [see Warnings and Precautions (5.13)]. Advise them not to drive or use machines if they experience these side effects during treatment.

Drug Interactions

Inform patients about the risk of drug interactions and the importance of providing a list of prescription and non-prescription drugs to their healthcare provider [see Drug Interactions (7)].

Distributed by: Hospira, Inc., Lake Forest, IL 60045 USA

PREMIERProRx® is a registered trademark of Premier Healthcare Alliance, L.P., used under license.

LAB-1470-3.0

Patient Information
Docetaxel (doe-se-TAKS-el) Injection
for intravenous use

What is the most important information I should know about Docetaxel Injection?

Docetaxel Injection can cause serious side effects, including death.

- The chance of death in people who receive Docetaxel Injection is higher if you:
  - have liver problems
  - receive high doses of Docetaxel Injection
  - have non-small cell lung cancer and have been treated with chemotherapy medicines that contain platinum
- Docetaxel Injection can affect your blood cells. Your healthcare provider should do routine blood tests during treatment with Docetaxel Injection. This will include regular checks of your white blood cell counts. If your white blood cells are too low, your healthcare provider may not treat you with Docetaxel Injection until you have enough white blood cells. People with low white blood cell counts can develop life-threatening infections. The earliest sign of infection may be fever. Follow your healthcare provider's instructions for how often to take your temperature during treatment with Docetaxel Injection. Call your healthcare provider right away if you have a fever.
- Swelling (inflammation) of the small intestine and colon. This can happen at any time during treatment and could lead to death as early as the first day you get symptoms. Tell your healthcare provider right away if you develop new or worse symptoms of intestinal problems, including stomach (abdominal) pain or tenderness or diarrhea, with or without fever.
- Severe allergic reactions are medical emergencies that can happen in people who receive Docetaxel Injection and can lead to death. You may be at higher risk of developing a severe allergic reaction to Docetaxel Injection if you are allergic to paclitaxel. Your healthcare provider will monitor you closely for allergic reactions during your Docetaxel Injection infusion.
  Tell your healthcare provider right away if you have any of these signs of a severe allergic reaction:
  - trouble breathing
  - sudden swelling of your face, lips, tongue, throat, or trouble swallowing
  - hives (raised bumps), rash, or redness all over your body
- Your body may hold too much fluid (severe fluid retention) during treatment with Docetaxel Injection. This can be life threatening. To decrease the chance of this happening, you must take another medicine, a corticosteroid, before each Docetaxel Injection treatment. You must take the corticosteroid exactly as your healthcare provider tells you. Tell your healthcare provider or nurse before your Docetaxel Injection treatment if you forgot to take your corticosteroid dose or do not take it as your healthcare provider tells you. Tell your healthcare provider right away if you have swelling in your legs or feet, weight gain or shortness of breath.
- Risk of new cancers. An increase in new (second) cancers has happened in people treated with Docetaxel Injection together with certain other anticancer treatments. This includes certain blood cancers, such as acute myeloid leukemia (AML), myelodysplastic syndrome (MDS), non-Hodgkin's Lymphoma (NHL), and kidney cancer.
  - Changes in blood counts due to leukemia and other blood disorders may occur years after treatment with Docetaxel Injection.
Your healthcare provider will check you for new cancers during and after your treatment with Docetaxel Injection.
- Severe skin problems.
  Tell your healthcare provider right away if you have any of these signs of a severe skin reaction:
  - redness and swelling of your arms and legs.
  - blistering, peeling, or bleeding on any part of your skin (including your lips, eyes, mouth, nose, genitals, hands or feet) with or without a rash. You may also have flu-like symptoms such as fever, chills, or muscle aches.
  - red, scaly rash all over your body with blisters, small red or white bumps under the skin that contain pus (pustules), and fever.

What is Docetaxel Injection?

Docetaxel Injection is a prescription anticancer medicine used to treat certain people with:

- breast cancer
- non-small cell lung cancer
- prostate cancer
- stomach cancer
- head and neck cancer

It is not known if Docetaxel Injection is effective in children.

Do not receive Docetaxel Injection if you:

- have a low white blood cell count.
- have had a severe allergic reaction to:
  - docetaxel, the active ingredient in Docetaxel Injection, or
  - any other medicines that contain polysorbate 80. Ask your healthcare provider or pharmacist if you are not sure.

See "What is the most important information I should know about Docetaxel Injection?" for the signs and symptoms of a severe allergic reaction.

See the end of this Patient Information for a complete list of the ingredients in Docetaxel Injection.

Before you receive Docetaxel Injection, tell your healthcare provider about all of your medical conditions, including if you:

- are allergic to any medicines, including paclitaxel. See "Do not receive Docetaxel Injection if you".
- have liver problems
- have kidney problems
- are pregnant or plan to become pregnant. Docetaxel Injection can harm your unborn baby. You should not become pregnant during treatment with Docetaxel Injection. Tell your healthcare provider if you become pregnant or you think you may be pregnant during treatment with Docetaxel Injection.
  Females who are able to become pregnant:
  - Your healthcare provider will check to see if you are pregnant before you start treatment with Docetaxel Injection.
  - You should use effective birth control (contraception) during treatment with Docetaxel Injection and for 2 months after the last dose.
Males with female partners who are able to become pregnant should use effective birth control during treatment with Docetaxel Injection and for 4 months after the last dose.
Talk to your healthcare provider if you have questions about birth control options that are right for you.
- are breastfeeding or plan to breastfeed. It is not known if Docetaxel Injection passes into your breast milk. Do not breastfeed during treatment with Docetaxel Injection and for 1 week after the last dose.

Tell your healthcare provider about all the medicines you take, including prescription and over-the-counter medicines, vitamins, and herbal supplements. Docetaxel Injection may affect the way other medicines work, and other medicines may affect the way Docetaxel Injection works.

Know the medicines you take. Keep a list of them to show your healthcare provider and pharmacist when you get a new medicine.

How will I receive Docetaxel Injection?

- Docetaxel Injection will be given to you as an intravenous (IV) injection into your vein, usually over 1 hour.
- Docetaxel Injection is usually given every 3 weeks.
- Your healthcare provider will decide how long you will receive treatment with Docetaxel Injection.
- Your healthcare provider will check your blood cell counts and other blood tests during your treatment with Docetaxel Injection to check for side effects of Docetaxel Injection.
- Your healthcare provider may stop your treatment, change the timing of your treatment, or change the dose of your treatment if you have certain side effects while receiving Docetaxel Injection.

What are the possible side effects of Docetaxel Injection?

Docetaxel Injection may cause serious side effects including death.

- See "What is the most important information I should know about Docetaxel Injection?"
- Neurologic problems. Neurologic symptoms are common in people who receive Docetaxel Injection but can be severe. Tell your healthcare provider right away if you have numbness, tingling, or burning in your hands or feet (peripheral neuropathy) or weakness of your legs, feet, arms, or hands (motor weakness).
- Vision problems including blurred vision or loss of vision. Tell your healthcare provider right away if you have any vision changes.
- Docetaxel Injection contains alcohol. The alcohol content in Docetaxel Injection may impair your ability to drive or use machinery right after receiving Docetaxel Injection. Consider whether you should drive, operate machinery or do other dangerous activities right after you receive Docetaxel Injection treatment.
- Tumor lysis syndrome (TLS). TLS is caused by the fast breakdown of cancer cells. TLS can cause kidney failure, the need for dialysis treatment, or heart problems, and may lead to death. Your healthcare provider will do blood tests to check for TLS when you first start treatment and during treatment with Docetaxel Injection. Tell your healthcare provider right away if you have any symptoms of TLS during treatment with Docetaxel Injection, including:

- nausea
- vomiting
- confusion
- shortness of breath

- irregular heartbeat
- dark or cloudy urine
- reduced amount of urine
- unusual tiredness
- muscle cramps

- You may experience side effects of Docetaxel Injection that may impair your ability to drive, use tools, or operate machines. If this happens, do not drive or use any tools or machines before discussing with your healthcare provider.

The most common side effects of Docetaxel Injection include:

- infections
- low white blood cells (help fight infections), low red blood cells (anemia), and low platelets (help blood to clot)
- allergic reactions (See "What is the most important information I should know about Docetaxel Injection?")
- changes in your sense of taste
- shortness of breath
- constipation
- decreased appetite
- changes in your fingernails or toenails
- swelling of your hands, face, or feet

- feeling weak or tired
- joint and muscle pain
- nausea and vomiting
- diarrhea
- mouth or lip sores
- hair loss: in some people, permanent hair loss has been reported
- redness of the eye, excess tearing
- skin reactions at the site of Docetaxel Injection administration such as increased skin pigmentation, redness, tenderness, swelling, warmth or dryness of the skin
- tissue damage if Docetaxel Injection leaks out of the vein into the tissues

Tell your healthcare provider if you have a fast or irregular heartbeat, severe shortness of breath, dizziness or fainting during your infusion. If any of these events occurs after your infusion, get medical help right away.

Docetaxel Injection may affect fertility in males. Talk to your healthcare provider if this is a concern for you.

These are not all of the possible side effects of Docetaxel Injection. For more information, ask your healthcare provider or pharmacist.

Call your healthcare provider for medical advice about side effects. You may report side effects to FDA at 1-800-FDA-1088.

General information about the safe and effective use of Docetaxel Injection.

Medicines are sometimes prescribed for purposes other than those listed in this Patient Information. You can ask your pharmacist or healthcare provider for information about Docetaxel Injection that is written for health professionals.

What are the ingredients in Docetaxel Injection?

Active ingredient: docetaxel

Inactive ingredients: (20 mg injection): polysorbate 80, citric acid monohydrate, and dehydrated alcohol.
Distributed by: Hospira, Inc., Lake Forest, IL 60045 USA
PREMIERProRx® is a registered trademark of Premier Healthcare Alliance, L.P., used under license.
LAB-1472-2.0

For more information, call 1-800-441-4100, or go to www.pfizer.com

This Patient Information has been approved by the U.S. Food and Drug Administration. Revised: May 2023

Every three-week injection of Docetaxel Injection for breast, non-small cell lung and stomach, and head and neck cancers

Take your oral corticosteroid medicine as your healthcare provider tells you.

Oral corticosteroid dosing:

Day 1

Date: _________

Time: ______ AM

_______ PM

Day 2

Date: _________

Time: ______ AM

_______ PM

(Docetaxel Injection Treatment Day)

Day 3

Date: _________

Time: ______ AM

_______ PM

Every three-week injection of Docetaxel Injection for prostate cancer

Take your oral corticosteroid medicine as your healthcare provider tells you.

Oral corticosteroid dosing:

Date: _________

Time: ___________

Date: _________

Time: ___________

(Docetaxel Injection Treatment Day)

Time: ___________

PRINCIPAL DISPLAY PANEL - 1 mL Vial Label

1 mL
Rx only
NDC 0409-4235-01

Docetaxel Injection, USP
20 mg/mL

Single-dose vial.
Discard unused portion.

For Intravenous Use only

Ready to add to infusion solution.
Check concentration prior to
preparation. See package insert
for complete instructions.

LOT

EXP

PRINCIPAL DISPLAY PANEL - 1 mL Vial Carton

20 mg/mL

1 x 1 mL
Single-dose vial
Discard unused portion.
NDC 0409-4235-01

Docetaxel
Injection, USP

20 mg/mL

For Intravenous Use only
Ready to add to
infusion solution
Caution: Hazardous Drug

Check concentration
prior to preparation.
See package insert for
complete instructions.

PRINCIPAL DISPLAY PANEL - 4 mL Vial Label

4 mL Multiple-dose Vial
Sterile
NDC 0409-5068-01

Docetaxel Injection, USP
80 mg/4 mL
(20 mg/mL)

For Intravenous Use only
Rx only

Ready to add to infusion solution. Check
concentration prior to preparation. See
package insert for complete instructions.

LOT
EXP

PRINCIPAL DISPLAY PANEL - 4 mL Vial Carton

80 mg/4 mL (20 mg/mL)

1 x 4 mL
Multiple-dose vial
NDC 0409-5068-01

Docetaxel
Injection, USP
80 mg/4 mL
(20 mg/mL)

For Intravenous Use only
Ready to add to
infusion solution
Caution: Hazardous Drug

Check concentration
prior to preparation.
See package insert for
complete instructions.

PRINCIPAL DISPLAY PANEL - 8 mL Vial Label

8 mL Multiple-dose Vial
Sterile
NDC 0409-0365-01

Docetaxel Injection, USP
160 mg/8 mL
(20 mg/mL)

For Intravenous Use only
Rx only

Ready to add to infusion solution. Check
concentration prior to preparation. See
package insert for complete instructions.

PRINCIPAL DISPLAY PANEL - 8 mL Vial Carton

160 mg/8 mL (20 mg/mL)

1 x 8 mL
Multiple-dose vial
NDC 0409-0365-01

Docetaxel
Injection, USP
160 mg/8 mL
(20 mg/mL)

For Intravenous Use only
Ready to add to
infusion solution
Caution: Hazardous Drug

Check concentration
prior to preparation.
See package insert for
complete instructions.